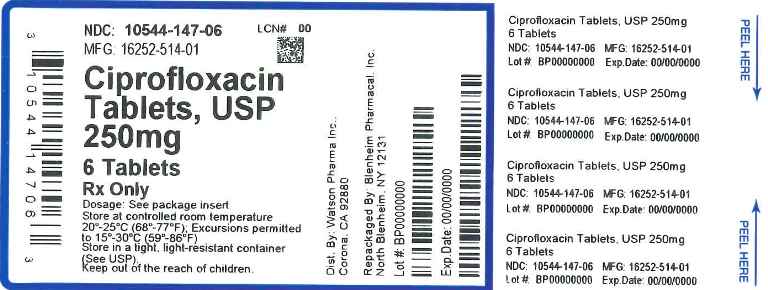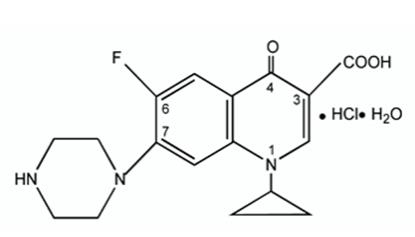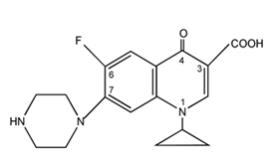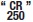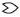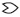 DRUG LABEL: Ciprofloxacin
NDC: 10544-147 | Form: TABLET, FILM COATED
Manufacturer: Blenheim Pharmacal, Inc.
Category: prescription | Type: HUMAN PRESCRIPTION DRUG LABEL
Date: 20151229

ACTIVE INGREDIENTS: CIPROFLOXACIN HYDROCHLORIDE 250 mg/1 1
INACTIVE INGREDIENTS: STARCH, CORN; CELLULOSE, MICROCRYSTALLINE; SILICON DIOXIDE; CROSPOVIDONE; MAGNESIUM STEARATE; POLYVINYL ALCOHOL; TALC; TITANIUM DIOXIDE; POLYETHYLENE GLYCOLS; WATER

Ciprofloxacin Tablets, USP

CIPROFLOXACIN TABLETS, USP

Rx Only

WARNING:

Fluoroquinolones, including ciprofloxacin hydrochloride, are associated with an increased risk of tendinitis and tendon rupture in all ages. This risk is further increased in older patients usually over 60 years of age, in patients taking corticosteroid drugs, and in patients with kidney, heart or lung transplants (see WARNINGS).

Fluoroquinolones, including ciprofloxacin hydrochloride, may exacerbate muscle weakness in persons with myasthenia gravis. Avoid ciprofloxacin hydrochloride in patients with known history of myasthenia gravis (see WARNINGS).

To reduce the development of drug-resistant bacteria and maintain the effectiveness of ciprofloxacin hydrochloride tablets and other antibacterial drugs, ciprofloxacin hydrochloride tablets should be used only to treat or prevent infections that are proven or strongly suspected to be caused by bacteria.

DESCRIPTION

Ciprofloxacin tablets, USP is a synthetic broad spectrum antimicrobial agent for oral administration. Ciprofloxacin hydrochloride, USP, a fluoroquinolone, is the monohydrochloride monohydrate salt of 1-cyclopropyl-6-fluoro-1,4-dihydro-4-oxo-7-(1-piperazinyl)-3-quinolinecarboxylic acid. It is a faintly yellowish to light yellow crystalline substance with a molecular weight of 385.8. Its molecular formula is C17H18FN3O3●ŸŸHClŸ●H2O and its chemical structure is as follows:

Ciprofloxacin, USP is 1-cyclopropyl-6-fluoro-1,4-dihydro-4-oxo-7-(1-piperazinyl)-3-quinolinecarboxylic acid. Its molecular formula is C17H18FN3O3 and its molecular weight is 331.4. It is a faintly yellowish to light yellow crystalline substance and its chemical structure is as follows:

Ciprofloxacin film-coated tablets are available in 250 mg, 500 mg and 750 mg (ciprofloxacin equivalent) strengths. Ciprofloxacin tablets, USP are white to off-white. The inactive ingredients are cornstarch, microcrystalline cellulose, silicon dioxide, crospovidone, magnesium stearate, polyvinyl alcohol, talc, titanium dioxide, polyethylene glycol and purified water.

CLINICAL PHARMACOLOGY

Absorption:

Ciprofloxacin given as an oral tablet is rapidly and well absorbed from the gastrointestinal tract after oral administration. The absolute bioavailability is approximately 70% with no substantial loss by first pass metabolism. Ciprofloxacin maximum serum concentrations and area under the curve are shown in the chart for the 250 mg to 1000 mg dose range.

Dose (mg) | Maximum Serum Concentration (mcg/mL) | Area Under Curve (AUC) (mcg•hr/mL)
250 | 1.2 | 4.8
500 | 2.4 | 11.6
750 | 4.3 | 20.2
1000 | 5.4 | 30.8

Maximum serum concentrations are attained 1 to 2 hours after oral dosing. Mean concentrations 12 hours after dosing with 250, 500, or 750 mg are 0.1, 0.2, and 0.4 mcg/mL, respectively. The serum elimination half-life in subjects with normal renal function is approximately 4 hours. Serum concentrations increase proportionately with doses up to 1000 mg.

A 500 mg oral dose given every 12 hours has been shown to produce an area under the serum concentration time curve (AUC) equivalent to that produced by an intravenous infusion of 400 mg ciprofloxacin given over 60 minutes every 12 hours. A 750 mg oral dose given every 12 hours has been shown to produce an AUC at steady-state equivalent to that produced by an intravenous infusion of 400 mg given over 60 minutes every 8 hours. A 750 mg oral dose results in a Cmax similar to that observed with a 400 mg IV dose. A 250 mg oral dose given every 12 hours produces an AUC equivalent to that produced by an infusion of 200 mg ciprofloxacin given every 12 hours.

Steady-state Pharmacokinetic Parameters
Following Multiple Oral and IV Doses
Parameters | 500 mg q12h, P.O. | 400 mg q12h, IV | 750 mg q12h, P.O. | 400 mg q8h, IV
AUC (mcg●hr/mL) | 13.7a | 12.7a | 31.6b | 32.9c
Cmax (mcg/mL) | 2.97 | 4.56 | 3.59 | 4.07
aAUC0-12h
bAUC 24h=AUC0-12h x 2
cAUC 24h=AUC0-8h x 3

Distribution

The binding of ciprofloxacin to serum proteins is 20 to 40% which is not likely to be high enough to cause significant protein binding interactions with other drugs.

After oral administration, ciprofloxacin is widely distributed throughout the body. Tissue concentrations often exceed serum concentrations in both men and women, particularly in genital tissue including the prostate. Ciprofloxacin is present in active form in the saliva, nasal and bronchial secretions, mucosa of the sinuses, sputum, skin blister fluid, lymph, peritoneal fluid, bile, and prostatic secretions. Ciprofloxacin has also been detected in lung, skin, fat, muscle, cartilage, and bone. The drug diffuses into the cerebrospinal fluid (CSF); however, CSF concentrations are generally less than 10% of peak serum concentrations. Low levels of the drug have been detected in the aqueous and vitreous humors of the eye.

Metabolism

Four metabolites have been identified in human urine which together account for approximately 15% of an oral dose. The metabolites have antimicrobial activity, but are less active than unchanged ciprofloxacin. Ciprofloxacin is an inhibitor of human cytochrome P450 1A2 (CYP1A2) mediated metabolism. Coadministration of ciprofloxacin with other drugs primarily metabolized by CYP1A2 results in increased plasma concentrations of these drugs and could lead to clinically significant adverse events of the coadministered drug (see CONTRAINDICATIONS, WARNINGS, PRECAUTIONS, Drug Interactions).

Excretion

The serum elimination half-life in subjects with normal renal function is approximately 4 hours. Approximately 40 to 50% of an orally administered dose is excreted in the urine as unchanged drug. After a 250 mg oral dose, urine concentrations of ciprofloxacin usually exceed 200 mcg/mL during the first two hours and are approximately 30 mcg/mL at 8 to 12 hours after dosing. The urinary excretion of ciprofloxacin is virtually complete within 24 hours after dosing. The renal clearance of ciprofloxacin, which is approximately 300 mL/minute, exceeds the normal glomerular filtration rate of 120 mL/minute. Thus, active tubular secretion would seem to play a significant role in its elimination. Co-administration of probenecid with ciprofloxacin results in about a 50% reduction in the ciprofloxacin renal clearance and a 50% increase in its concentration in the systemic circulation.

Although bile concentrations of ciprofloxacin are several fold higher than serum concentrations after oral dosing, only a small amount of the dose administered is recovered from the bile as unchanged drug. An additional 1 to 2% of the dose is recovered from the bile in the form of metabolites. Approximately 20 to 35% of an oral dose is recovered from the feces within 5 days after dosing. This may arise from either biliary clearance or transintestinal elimination.

Drug-Drug Interactions

When ciprofloxacin hydrochloride tablets are given concomitantly with food, there is a delay in the absorption of the drug, resulting in peak concentrations that occur closer to 2 hours after dosing rather than 1 hour. The overall absorption of ciprofloxacin hydrochloride tablets, however, is not substantially affected. Concurrent administration of antacids containing magnesium hydroxide or aluminum hydroxide may reduce the bioavailability of ciprofloxacin by as much as 90%. (See PRECAUTIONS.)

The serum concentrations of ciprofloxacin and metronidazole were not altered when these two drugs were given concomitantly.

Concomitant administration with tizanidine is contraindicated. (See CONTRAINDICATIONS).

Concomitant administration of ciprofloxacin with theophylline decreases the clearance of theophylline resulting in elevated serum theophylline levels and increased risk of a patient developing CNS or other adverse reactions. Ciprofloxacin also decreases caffeine clearance and inhibits the formation of paraxanthine after caffeine administration. (See WARNINGS: PRECAUTIONS.)

Special Populations

Pharmacokinetic studies of the oral (single dose) form of ciprofloxacin indicate that plasma concentrations of ciprofloxacin are higher in elderly subjects (> 65 years) as compared to young adults. Although the Cmax is increased 16 to 40%, the increase in mean AUC is approximately 30%, and can be at least partially attributed to decreased renal clearance in the elderly. Elimination half-life is only slightly (~20%) prolonged in the elderly. These differences are not considered clinically significant. (See PRECAUTIONS: Geriatric Use.)

Patients with Renal Impairment
In patients with reduced renal function, the half-life of ciprofloxacin is slightly prolonged. Dosage adjustments may be required. (See DOSAGE AND ADMINISTRATION.)

Patients with Hepatic Impairment
In preliminary studies in patients with stable chronic liver cirrhosis, no significant changes in ciprofloxacin pharmacokinetics have been observed. The kinetics of ciprofloxacin in patients with acute hepatic insufficiency, however, have not been fully elucidated.

Pediatrics
Following a single oral dose of 10 mg/kg ciprofloxacin suspension to 16 children ranging in age from 4 months to 7 years, the mean Cmax was 2.4 mcg/mL (range: 1.5 to 3.4 mcg/mL) and the mean AUC was 9.2 mcg*h/mL (range: 5.8 to 14.9 mcg*h/mL). There was no apparent age-dependence, and no notable increase in Cmax or AUC upon multiple dosing (10 mg/kg TID). In children with severe sepsis who were given intravenous ciprofloxacin (10 mg/kg as a 1-hour infusion), the mean Cmax was 6.1 mcg/mL (range: 4.6 to 8.3 mcg/mL) in 10 children less than 1 year of age; and 7.2 mcg/mL (range: 4.7 to 11.8 mcg/mL) in 10 children between 1 and 5 years of age. The AUC values were 17.4 mcg*h/mL (range: 11.8 to 32.0 mcg*h/mL) and 16.5 mcg*h/mL (range: 11.0 to 23.8 mcg*h/mL) in the respective age groups. These values are within the range reported for adults at therapeutic doses. Based on population pharmacokinetic analysis of pediatric patients with various infections, the predicted mean half-life in children is approximately 4 to 5 hours, and the bioavailability of the oral suspension is approximately 60%.

MICROBIOLOGY

Mechanism of Action

The bactericidal action of ciprofloxacin results from inhibition of the enzymes topoisomerase II (DNA gyrase) and topoisomerase IV (both Type II topoisomerases), which are required for bacterial DNA replication, transcription, repair, and recombination.

Mechanism of Resistance

The mechanism of action of fluoroquinolones, including ciprofloxacin, is different from that of penicillins, cephalosporins, aminoglycosides, macrolides, and tetracyclines; therefore, microorganisms resistant to these classes of drugs may be susceptible to ciprofloxacin. Resistance to fluoroquinolones occurs primarily by either mutations in the DNA gyrases, decreased outer membrane permeability, or drug efflux. In vitro resistance to ciprofloxacin develops slowly by multiple step mutations. Resistance to ciprofloxacin due to spontaneous mutations occurs at a general frequency of between < 10^-9 to 1x10^-6.

Cross Resistance

There is no known cross-resistance between ciprofloxacin and other classes of antimicrobials.

Ciprofloxacin has been shown to be active against most isolates of the following bacteria, both in vitro and in clinical infections as described in the INDICATIONS AND USAGE section of the package insert for ciprofloxacin hydrochloride tablets.

Gram-positive bacteria

Enterococcus faecalis (vancomycin-susceptible isolates only)

Staphylococcus aureus (methicillin-susceptible isolates only)

Staphylococcus epidermidis (methicillin-susceptible isolates only)

Staphylococcus saprophyticus

Streptococcus pneumoniae (penicillin-susceptible isolates only)

Streptococcus pyogenes

Gram-negative bacteria
Campylobacter jejuni | Proteus mirabilis
Citrobacter koseri (diversus) | Proteus vulgaris
Citrobacter freundii | Providencia rettgeri
Enterobacter cloacae | Providencia stuartii
Escherichia coli | Pseudomonas aeruginosa
Haemophilus influenzae | Salmonella typhi
Haemophilus parainfluenzae | Serratia marcescens
Klebsiella pneumoniae | Shigella boydii
Moraxella catarrhalis | Shigella dysenteriae
Morganella morganii | Shigella flexneri
Neisseria gonorrhoeae | Shigella sonnei

Ciprofloxacin has been shown to be active against Bacillus anthracis both in vitro and by use of serum levels as a surrogate marker (see INDICATIONS AND USAGEand INHALATIONAL ANTHRAX -ADDITIONAL INFORMATION).

The following in vitro data are available, but their clinical significance is unknown. At least 90 percent of the following bacteria exhibit an in vitro minimum inhibitory concentration (MIC) less than or equal to the susceptible breakpoint for ciprofloxacin (≤1 mcg/mL). However, the efficacy of ciprofloxacin in treating clinical infections due to these bacteria has not been established in adequate and well-controlled clinical trials.

Gram-positive bacteria

Staphylococcus haemolyticus (methicillin-susceptible isolates only)

Staphylococcus hominis (methicillin-susceptible isolates only)

Bacillus anthracis

Gram-negative bacteria
Acinetobacter lwoffi | Pasteurella multocida
Aeromonas hydrophila | Salmonella enteritidis
Edwardsiella tarda | Vibrio cholerae
Enterobacter aerogenes | Vibrio parahaemolyticus
Klebsiella oxytoca | Vibrio vulnificus
Legionella pneumophila | Yersinia enterocolitica

Susceptibility Test Methods

When available, the clinical microbiology laboratory should provide the results of in vitro susceptibility test results for antimicrobial drug products used in resident hospitals to the physician as periodic reports that describe the susceptibility profile of nosocomial and community-acquired pathogens. These reports should aid the physician in selecting an antibacterial drug product for treatment.

- Dilution Techniques: Quantitative methods are used to determine antimicrobial minimum inhibitory concentrations (MICs). These MICs provide estimates of the susceptibility of bacteria to antimicrobial compounds. The MICs should be determined using a standardized test method (broth and/or agar).^1,3,4 The MIC values should be interpreted according to criteria provided in Table 1.
- Diffusion Techniques: Quantitative methods that require measurement of zone diameters can also provide reproducible estimates of the susceptibility of bacteria to antimicrobial compounds. The zone size provides an estimate of the susceptibility of bacteria to antimicrobial compounds. The zone size should be determined using a standardized test method.^2,3,4 This procedure uses paper disks impregnated with 5 mcg ciprofloxacin to test the susceptibility of bacteria to ciprofloxacin. The disc diffusion interpretive criteria are provided in Table 1.

Table 1: Susceptibility Test Interpretive Criteria for Ciprofloxacin
 | MIC (mcg/mL) |  |  | Zone Diameter (mm)
Bacteria | S | I | R | S | I | R
Enterobacteriaceae | ≤1 | 2 | ≥4 | ≥21 | 16 to 20 | ≤15
Enterococcus faecalis | ≤1 | 2 | ≥4 | ≥21 | 16 to 20 | ≤15
Staphylococcus aureus | ≤1 | 2 | ≥4 | ≥21 | 16 to 20 | ≤15
Staphylococcus epidermidis | ≤1 | 2 | ≥4 | ≥21 | 16 to 20 | ≤15
Staphylococcus saprophyticus | ≤1 | 2 | ≥4 | ≥21 | 16 to 20 | ≤15
Pseudomonas aeruginosa | ≤1 | 2 | ≥4 | ≥21 | 16 to 20 | ≤15
Haemophilus influenzaea | ≤1 | - | - | ≥21 | - | -
Haemophilus parainfluenzaea | ≤1 | - | - | ≥21 | - | -
Salmonella typhi | ≤0.06 | 0.12 to 0.5 | >1 | ≥31 | 21 to 30 | ≤20
Streptococcus pneumoniae | ≤1 | 2 | ≥4 | ≥21 | 16 to 20 | ≤15
Streptococcus pyogenes | ≤1 | 2 | ≥4 | ≥21 | 16 to 20 | ≤15
Neisseria gonorrhoeae | ≤0.06 | 0.12 to 0.5 | ≥1 | ≥41 | 28 to 40 | ≤27
Bacillus anthracisa | ≤0.25 | - | - | - | - | -
S=Susceptible, I=Intermediate, and R=Resistant.
a The current absence of data on resistant isolates precludes defining any results other than “Susceptible”. If isolates yield MIC results other than susceptible, they should be submitted to a reference laboratory for further testing.

A report of “Susceptible” indicates that the antimicrobial is likely to inhibit growth of the pathogen if the antimicrobial compound reaches the concentrations at the site of infection necessary to inhibit growth of the pathogen. A report of “Intermediate” indicates that the result should be considered equivocal, and, if the microorganism is not fully susceptible to alternative, clinically feasible drugs, the test should be repeated. This category implies possible clinical applicability in body sites where the drug is physiologically concentrated or in situations where high dosage of drug can be used. This category also provides a buffer zone that prevents small uncontrolled technical factors from causing major discrepancies in interpretation. A report of “Resistant” indicates that the antimicrobial is not likely to inhibit growth of the pathogen if the antimicrobial compound reaches the concentrations usually achievable at the infection site; other therapy should be selected.

- Quality Control: Standardized susceptibility test procedures require the use of laboratory controls to monitor the accuracy and precision of supplies and reagents used in the assay, and the techniques of the individuals performing the test.^1,2,3,4 Standard ciprofloxacin powder should provide the following range of MIC values noted in Table 2. For the diffusion technique using the ciprofloxacin 5 mcg disk the criteria in Table 2 should be achieved.

Table 2: Acceptable Quality Control Ranges for Ciprofloxacin
Bacteria | MIC range (mcg/mL) | Zone Diameter (mm)
Enterococcus faecalis ATCC 29212 | 0.25 to 2 | -
Escherichia coli ATCC 25922 | 0.004 to 0.015 | 30 to 40
Haemophilus influenzae ATCC 49247 | 0.004 to 0.03 | 34 to 42
Pseudomonas aeruginosa ATCC 27853 | 0.25 to 1 | 25 to 33
Staphylococcus aureus ATCC29213 | 0.12 to 0.5 | -
Staphylococcus aureus ATCC25923 | - | 22 to 30
Neisseria gonorrhoeae ATCC 49226 | 0.001 to 0.008 | 48 to 58
Campylobacter jejuni ATCC 33560 | 0.06 to 0.25 and 0.03 to 0.12

INDICATIONS AND USAGE

Ciprofloxacin tablets, USP are indicated for the treatment of infections caused by susceptible isolates of the designated microorganisms in the conditions and patient populations listed below. Please see DOSAGE AND ADMINISTRATIONfor specific recommendations.

Adult Patients

Urinary Tract Infections caused by Escherichia coli, Klebsiella pneumoniae, Enterobacter cloacae, Serratia marcescens, Proteus mirabilis, Providencia rettgeri, Morganella morganii, Citrobacter koseri (diversus), Citrobacter freundii, Pseudomonas aeruginosa, methicillin-susceptible Staphylococcus epidermidis, Staphylococcus saprophyticus, or vancomycin-susceptible Enterococcus faecalis.

Acute Uncomplicated Cystitis in Females caused by Escherichia coli or Staphylococcus saprophyticus.

Chronic Bacterial Prostatitis caused by Escherichia coli or Proteus mirabilis.

Lower Respiratory Tract Infections caused by Escherichia coli, Klebsiella pneumoniae, Enterobacter cloacae, Proteus mirabilis, Pseudomonas aeruginosa, Haemophilus influenzae, Haemophilus parainfluenzae, or penicillin-susceptible Streptococcus pneumoniae.* Also, Moraxella catarrhalis for the treatment of acute exacerbations of chronic bronchitis.

*Ciprofloxacin is not a drug of first choice in the treatment of presumed or confirmed pneumonia secondary to Streptococcus pneumoniae.

Acute Sinusitis caused by Haemophilus influenzae, penicillin-susceptible Streptococcus pneumoniae, or Moraxella catarrhalis.

Skin and Skin Structure Infections caused by Escherichia coli, Klebsiella pneumoniae, Enterobacter cloacae, Proteus mirabilis, Proteus vulgaris, Providencia stuartii, Morganella morganii, Citrobacter freundii, Pseudomonas aeruginosa, methicillin-susceptible Staphylococcus aureus, methicillin-susceptible Staphylococcus epidermidis, or Streptococcus pyogenes.

Bone and Joint Infections caused by Enterobacter cloacae, Serratia marcescens, or Pseudomonas aeruginosa.

Complicated Intra-Abdominal Infections (used in combination with metronidazole) caused by Escherichia coli, Pseudomonas aeruginosa, Proteus mirabilis, Klebsiella pneumoniae, or Bacteroides fragilis.

Infectious Diarrhea caused by Escherichia coli (enterotoxigenic isolates), Campylobacter jejuni, Shigella boydii†, Shigella dysenteriae, Shigella flexneri or Shigella sonnei†when antibacterial therapy is indicated.

†Although treatment of infections due to this organism in this organ system demonstrated a clinically significant outcome, efficacy was studied in fewer than 10 patients.

Typhoid Fever (Enteric Fever) caused by Salmonella typhi.

NOTE: The efficacy of ciprofloxacin in the eradication of the chronic typhoid carrier state has not been demonstrated.

Uncomplicated Cervical and Urethral Gonorrhea due to Neisseria gonorrhoeae.

Pediatric Patients (1 to 17 years of age)

Complicated Urinary Tract Infections and Pyelonephritis due to Escherichia coli.

NOTE: Although effective in clinical trials, ciprofloxacin is not a drug of first choice in the pediatric population due to an increased incidence of adverse events compared to controls, including events related to joints and/or surrounding tissues. (See WARNINGS, PRECAUTIONS, Pediatric Use, ADVERSE REACTIONSand CLINICAL STUDIES.) Ciprofloxacin, like other fluoroquinolones, is associated with arthropathy and histopathological changes in weight-bearing joints of juvenile animals. (See ANIMAL PHARMACOLOGY.)

Adult and Pediatric Patients

Inhalational Anthrax (post-exposure): To reduce the incidence or progression of disease following exposure to aerosolized Bacillus anthracis.

Ciprofloxacin serum concentrations achieved in humans served as a surrogate endpoint reasonably likely to predict clinical benefit and provided the initial basis for approval of this indication.^5 Supportive clinical information for ciprofloxacin for anthrax post-exposure prophylaxis was obtained during the anthrax bioterror attacks of October 2001. (See also, INHALATIONAL ANTHRAX - ADDITIONAL INFORMATION).

If anaerobic organisms are suspected of contributing to the infection, appropriate therapy should be administered. Appropriate culture and susceptibility tests should be performed before treatment in order to isolate and identify organisms causing infection and to determine their susceptibility to ciprofloxacin. Therapy with ciprofloxacin tablets, USP may be initiated before results of these tests are known; once results become available appropriate therapy should be continued. As with other drugs, some isolates of Pseudomonas aeruginosa may develop resistance fairly rapidly during treatment with ciprofloxacin. Culture and susceptibility testing performed periodically during therapy will provide information not only on the therapeutic effect of the antimicrobial agent but also on the possible emergence of bacterial resistance.

To reduce the development of drug-resistant bacteria and maintain the effectiveness of ciprofloxacin tablets, USP and other antibacterial drugs, ciprofloxacin tablets, USP should be used only to treat or prevent infections that are proven or strongly suspected to be caused by susceptible bacteria.When culture and susceptibility information are available, they should be considered in selecting or modifying antibacterial therapy. In the absence of such data, local epidemiology and susceptibility patterns may contribute to the empiric selection of therapy.

CONTRAINDICATIONS

Ciprofloxacin is contraindicated in persons with a history of hypersensitivity to ciprofloxacin, any member of the quinolone class of antimicrobial agents, or any of the product components (see DESCRIPTION).

Concomitant administration with tizanidine is contraindicated. (See PRECAUTIONS: Drug Interactions.)

WARNINGS

Tendinopathy and Tendon Rupture

Fluoroquinolones, including ciprofloxacin hydrochloride, are associated with an increased risk of tendinitis and tendon rupture in all ages. This adverse reaction most frequently involves the Achilles tendon, and rupture of the Achilles tendon may require surgical repair. Tendinitis and tendon rupture in the rotator cuff (the shoulder), the hand, the biceps, the thumb, and other tendon sites have also been reported. The risk of developing fluoroquinolone-associated tendinitis and tendon rupture is further increased in older patients usually over 60 years of age, in patients taking corticosteroid drugs, and in patients with kidney, heart or lung transplants. Factors, in addition to age and corticosteroid use, that may independently increase the risk of tendon rupture include strenuous physical activity, renal failure, and previous tendon disorders such as rheumatoid arthritis. Tendinitis and tendon rupture have also occurred in patients taking fluoroquinolones who do not have the above risk factors. Inflammation and tendon rupture can occur, sometimes bilaterally, even within the first 48 hours, during or after completion of therapy; cases occurring up to several months after completion of therapy have been reported. Ciprofloxacin hydrochloride should be used with caution in patients with a history of tendon disorders. Ciprofloxacin hydrochloride should be discontinued if the patient experiences pain, swelling, inflammation or rupture of a tendon. Patients should be advised to rest at the first sign of tendinitis or tendon rupture, and to contact their healthcare provider regarding changing to a non-quinolone antimicrobial drug.

Exacerbation of Myasthenia Gravis

Fluoroquinolones, including ciprofloxacin hydrochloride, have neuromuscular blocking activity and may exacerbate muscle weakness in persons with myasthenia gravis. Postmarketing serious adverse events, including deaths and requirement for ventilatory support, have been associated with fluoroquinolone use in persons with myasthenia gravis. Avoid ciprofloxacin hydrochloride in patients with known history of myasthenia gravis. (See PRECAUTIONS: Information for Patientsand ADVERSE REACTIONS: Postmarketing Adverse Event Reports.)

Pregnant Women

THE SAFETY AND EFFECTIVENESS OF CIPROFLOXACIN IN PREGNANT AND LACTATING WOMEN HAVE NOT BEEN ESTABLISHED. (See PRECAUTIONS: Pregnancy, and Nursing Motherssubsections.)

Hypersensitivity Reactions

Serious and occasionally fatal hypersensitivity (anaphylactic) reactions, some following the first dose, have been reported in patients receiving quinolone therapy. Some reactions were accompanied by cardiovascular collapse, loss of consciousness, tingling, pharyngeal or facial edema, dyspnea, urticaria, and itching. Only a few patients had a history of hypersensitivity reactions. Serious anaphylactic reactions require immediate emergency treatment with epinephrine. Oxygen, intravenous steroids, and airway management, including intubation, should be administered as indicated.

Other Serious and Sometimes Fatal Reactions

Other serious and sometimes fatal events, some due to hypersensitivity, and some due to uncertain etiology, have been reported rarely in patients receiving therapy with quinolones, including ciprofloxacin. These events may be severe and generally occur following the administration of multiple doses. Clinical manifestations may include one or more of the following:

- Fever, rash, or severe dermatologic reactions (for example, toxic epidermal necrolysis, Stevens-Johnson syndrome);
- Vasculitis; arthralgia; myalgia; serum sickness;
- Allergic pneumonitis;
- Interstitial nephritis; acute renal insufficiency or failure;
- Hepatitis; jaundice; acute hepatic necrosis or failure;
- Anemia, including hemolytic and aplastic; thrombocytopenia, including thrombotic thrombocytopenic purpura; leukopenia; agranulocytosis; pancytopenia; and/or other hematologic abnormalities.

The drug should be discontinued immediately at the first appearance of a skin rash, jaundice, or any other sign of hypersensitivity and supportive measures instituted (see PRECAUTIONS: Information for Patientsand ADVERSE REACTIONS).

Hepatobiliary System

Cases of severe hepatotoxicity, including hepatic necrosis, life-threatening hepatic failure, and fatal events, have been reported with ciprofloxacin. Acute liver injury is rapid in onset (range 1 to 39 days), and is often associated with hypersensitivity. The pattern of injury can be hepatocellular, cholestatic or mixed. Most patients with fatal outcomes were older than 55 years old. In the event of any signs and symptoms of hepatitis (such as anorexia, jaundice, dark urine, pruritus, or tender abdomen), treatment should be discontinued immediately (see ADVERSE REACTIONS).

There can be a temporary increase in transaminases, alkaline phosphatase, or cholestatic jaundice, especially in patients with previous liver damage, who are treated with ciprofloxacin (see ADVERSE REACTIONS).

Theophylline

SERIOUS AND FATAL REACTIONS HAVE BEEN REPORTED IN PATIENTS RECEIVING CONCURRENT ADMINISTRATION OF CIPROFLOXACIN AND THEOPHYLLINE. These reactions have included cardiac arrest, seizure, status epilepticus, and respiratory failure. Although similar serious adverse effects have been reported in patients receiving theophylline alone, the possibility that these reactions may be potentiated by ciprofloxacin cannot be eliminated. If concomitant use cannot be avoided, serum levels of theophylline should be monitored and dosage adjustments made as appropriate.

Central Nervous System Effects

Convulsions, increased intracranial pressure (including pseudotumor cerebri), and toxic psychosis have been reported in patients receiving fluoroquinolones, including ciprofloxacin. Ciprofloxacin may also cause central nervous system (CNS) events including: dizziness, confusion, tremors, hallucinations, depression, and, rarely, psychotic reactions have progressed to suicidal ideations/thoughts and self-injurious behavior such as attempted or completed suicide. These reactions may occur following the first dose. If these reactions occur in patients receiving ciprofloxacin, the drug should be discontinued, patients should be advised to inform their healthcare provider immediately and appropriate measures instituted. Ciprofloxacin hydrochloride, like other fluoroquinolones, is known to trigger seizures or lower the seizure threshold. As with all fluoroquinolones, ciprofloxacin should be used with caution in epileptic patients and patients with known or suspected CNS disorders that may predispose to seizures or lower the seizure threshold (for example, severe cerebral arteriosclerosis, previous history of convulsion, reduced cerebral blood flow, altered brain structure, or stroke), or in the presence of other risk factors that may predispose to seizures or lower the seizure threshold (for example, certain drug therapy, renal dysfunction). Ciprofloxacin hydrochloride should only be used where the benefits of treatment exceed the risks, since these patients are endangered because of possible undesirable CNS side effects. Cases of status epilepticus have been reported. If seizures occur, ciprofloxacin should be discontinued. (See PRECAUTIONS: General, Information for Patients, Drug Interactionsand ADVERSE REACTIONS.)

Clostridium difficile-associated diarrhea (CDAD) has been reported with use of nearly all antibacterial agents, including ciprofloxacin hydrochloride, and may range in severity from mild diarrhea to fatal colitis. Treatment with antibacterial agents alters the normal flora of the colon leading to overgrowth of C. difficile.

C. difficile produces toxins A and B which contribute to the development of CDAD. Hypertoxin producing isolates of C. difficile cause increased morbidity and mortality, as these infections can be refractory to antimicrobial therapy and may require colectomy. CDAD must be considered in all patients who present with diarrhea following antibiotic use. Careful medical history is necessary since CDAD has been reported to occur over two months after the administration of antibacterial agents.

If CDAD is suspected or confirmed, ongoing antibiotic use not directed against C. difficile may need to be discontinued. Appropriate fluid and electrolyte management, protein supplementation, antibiotic treatment of C. difficile, and surgical evaluation should be instituted as clinically indicated.

Peripheral Neuropathy

Cases of sensory or sensorimotor axonal polyneuropathy affecting small and/or large axons resulting in paresthesias, hypoesthesias, dysesthesias and weakness have been reported in patients receiving fluoroquinolones, including ciprofloxacin. Symptoms may occur soon after initiation of ciprofloxacin hydrochloride and may be irreversible. Ciprofloxacin should be discontinued immediately if the patient experiences symptoms of peripheral neuropathy including pain, burning, tingling, numbness, and/or weakness, other alterations in sensations including light touch, pain, temperature, position sense and vibratory sensation.

Musculoskeletal Disorders in Pediatric Patients and Arthropathic Effects in Animals

Ciprofloxacin should be used in pediatric patients (less than 18 years of age) only for infections listed in the INDICATIONS AND USAGE section. An increased incidence of adverse events compared to controls, including events related to joints and/or surrounding tissues, has been observed. (See ADVERSE REACTIONS.)

In pre-clinical studies, oral administration of ciprofloxacin caused lameness in immature dogs. Histopathological examination of the weight-bearing joints of these dogs revealed permanent lesions of the cartilage. Related quinolone-class drugs also produce erosions of cartilage of weight-bearing joints and other signs of arthropathy in immature animals of various species. (See ANIMAL PHARMACOLOGY.)

Prolongation of the QT Interval

Some fluoroquinolones, including ciprofloxacin, have been associated with prolongation of the QT interval on the electrocardiogram and infrequent cases of arrhythmia. Rare cases of torsade de pointes have been spontaneously reported during postmarketing surveillance in patients receiving fluoroquinolones, including ciprofloxacin. Ciprofloxacin should be avoided in patients with known prolongation of the QT interval, risk factors for QT prolongation or torsade de pointes (for example, congenital long QT syndrome, uncorrected electrolyte imbalance, such as hypokalemia or hypomagnesemia and cardiac disease, such as heart failure, myocardial infarction, or bradycardia), and patients receiving Class IA antiarrhythmic agents (quinidine, procainamide), or Class III antiarrhythmic agents (amiodarone, sotalol), tricyclic antidepressants, macrolides, and antipsychotics. Elderly patients may also be more susceptible to drug-associated effects on the QT interval. (See PRECAUTIONS, Drug Interactions and Geriatric Use.)

Cytochrome P450 (CYP450) Drug Interactions

Ciprofloxacin is an inhibitor of the hepatic CYP1A2 enzyme pathway. Coadministration of ciprofloxacin and other drugs primarily metabolized by CYP1A2 (for example, theophylline, methylxanthines, caffeine, tizanidine, ropinirole, clozapine, olanzapine) results in increased plasma concentrations of the coadministered drug and could lead to clinically significant pharmacodynamic side effects of the coadministered drug (See PRECAUTIONS, Drug Interactions).

Syphilis

Ciprofloxacin has not been shown to be effective in the treatment of syphilis. Antimicrobial agents used in high dose for short periods of time to treat gonorrhea may mask or delay the symptoms of incubating syphilis. All patients with gonorrhea should have a serologic test for syphilis at the time of diagnosis. Patients treated with ciprofloxacin should have a follow-up serologic test for syphilis after three months.

PRECAUTIONS

General

Crystals of ciprofloxacin have been observed rarely in the urine of human subjects but more frequently in the urine of laboratory animals, which is usually alkaline. (See ANIMAL PHARMACOLOGY.) Crystalluria related to ciprofloxacin has been reported only rarely in humans because human urine is usually acidic. Alkalinity of the urine should be avoided in patients receiving ciprofloxacin. Patients should be well hydrated to prevent the formation of highly concentrated urine.

Central Nervous System

Quinolones, including ciprofloxacin, may also cause central nervous system (CNS) events, including: nervousness, agitation, insomnia, anxiety, nightmares or paranoia. (See WARNINGS, Information for Patients, and Drug Interactions.)

Renal Impairment

Alteration of the dosage regimen is necessary for patients with impairment of renal function. (See DOSAGE AND ADMINISTRATION.)

Photosensitivity/Phototoxicity

Moderate to severe photosensitivity/phototoxicity reactions, the latter of which may manifest as exaggerated sunburn reactions (for example, burning, erythema, exudation, vesicles, blistering, edema) involving areas exposed to light (typically the face, “V” area of the neck, extensor surfaces of the forearms, dorsa of the hands), can be associated with the use of quinolones after sun or UV light exposure. Therefore, excessive exposure to these sources of light should be avoided. Drug therapy should be discontinued if phototoxicity occurs (See ADVERSE REACTIONS/Postmarketing Adverse Event Reports).

As with any potent drug, periodic assessment of organ system functions, including renal, hepatic, and hematopoietic function, is advisable during prolonged therapy.

Prescribing ciprofloxacin hydrochloride tablets in the absence of a proven or strongly suspected bacterial infection or a prophylactic indication is unlikely to provide benefit to the patient and increases the risk of the development of drug-resistant bacteria.

Information for Patients

Patients should be advised:

- To contact their healthcare provider if they experience pain, swelling, or inflammation of a tendon, or weakness or inability to use one of their joints; rest and refrain from exercise; and discontinue ciprofloxacin hydrochloride treatment. The risk of severe tendon disorder with fluoroquinolones is higher in older patients usually over 60 years of age, in patients taking corticosteroid drugs, and in patients with kidney, heart or lung transplants.
- That fluoroquinolones like ciprofloxacin hydrochloride may cause worsening of myasthenia gravis symptoms, including muscle weakness and breathing problems. Patients should call their healthcare provider right away if they have any worsening muscle weakness or breathing problems.
- That antibacterial drugs including ciprofloxacin hydrochloride tablets should only be used to treat bacterial infections. They do not treat viral infections (for example, the common cold). When ciprofloxacin hydrochloride tablets are prescribed to treat a bacterial infection, patients should be told that although it is common to feel better early in the course of therapy, the medication should be taken exactly as directed. Skipping doses or not completing the full course of therapy may (1) decrease the effectiveness of the immediate treatment and (2) increase the likelihood that bacteria will develop resistance and will not be treatable by ciprofloxacin hydrochloride tablets or other antibacterial drugs in the future.
- That ciprofloxacin may be taken with or without meals and to drink fluids liberally. As with other quinolones, concurrent administration of ciprofloxacin with magnesium/aluminum antacids, polymeric phosphate binders (for example, sevelamer, lanthanum carbonate) or sucralfate, Videx® (didanosine) chewable/buffered tablets or pediatric powder, other highly buffered drugs, or with other products containing calcium, iron or zinc should be avoided. Ciprofloxacin may be taken two hours before or six hours after taking these products. Ciprofloxacin should not be taken with dairy products (like milk or yogurt) or calcium-fortified juices alone since absorption of ciprofloxacin may be significantly reduced; however, ciprofloxacin may be taken with a meal that contains these products.
- That ciprofloxacin may be associated with hypersensitivity reactions, even following a single dose, and to discontinue the drug at the first sign of a skin rash or other allergic reaction.
- That photosensitivity/phototoxicity has been reported in patients receiving quinolones. Patients should minimize or avoid exposure to natural or artificial sunlight (tanning beds or UVA/B treatment) while taking quinolones. If patients need to be outdoors while using quinolones, they should wear loose-fitting clothes that protect skin from sun exposure and discuss other sun protection measures with their physician. If a sunburn-like reaction or skin eruption occurs, patients should contact their physician.
- That peripheral neuropathies have been associated with ciprofloxacin use, that symptoms may occur soon after initiation of therapy and may be irreversible. If symptoms of peripheral neuropathy including pain, burning, tingling, numbness and/or weakness develop, patients should immediately discontinue ciprofloxacin hydrochloride and contact their physician.
- That ciprofloxacin may cause dizziness and lightheadedness; therefore, patients should know how they react to this drug before they operate an automobile or machinery or engage in activities requiring mental alertness or coordination.
- That ciprofloxacin increases the effects of tizanidine (Zanaflex®). Patients should not use ciprofloxacin if they are already taking tizanidine.
- That ciprofloxacin may increase the effects of theophylline and caffeine. There is a possibility of caffeine accumulation when products containing caffeine are consumed while taking quinolones.
- That convulsions have been reported in patients receiving quinolones, including ciprofloxacin, and to notify their physician before taking this drug if there is a history of this condition.
- That ciprofloxacin has been associated with an increased rate of adverse events involving joints and surrounding tissue structures (like tendons) in pediatric patients (less than 18 years of age). Parents should inform their child’s physician if the child has a history of joint-related problems before taking this drug. Parents of pediatric patients should also notify their child’s physician of any joint-related problems that occur during or following ciprofloxacin therapy. (See WARNINGS, PRECAUTIONS, Pediatric Use and ADVERSE REACTIONS.)
- That diarrhea is a common problem caused by antibiotics which usually ends when the antibiotic is discontinued. Sometimes after starting treatment with antibiotics, patients can develop watery and bloody stools (with or without stomach cramps and fever) even as late as two or more months after having taken the last dose of the antibiotic. If this occurs, patients should contact their physician as soon as possible.

Drug Interactions

Tizanidine
In a pharmacokinetic study, systemic exposure of tizanidine (4 mg single dose) was significantly increased (Cmax 7-fold, AUC 10-fold) when the drug was given concomitantly with ciprofloxacin (500 mg BID for 3 days). The hypotensive and sedative effects of tizanidine were also potentiated. Concomitant administration of tizanidine and ciprofloxacin is contraindicated. (See CONTRAINDICATIONS.)

Theophylline
As with some other quinolones, concurrent administration of ciprofloxacin with theophylline may lead to elevated serum concentrations of theophylline and prolongation of its elimination half-life. This may result in increased risk of theophylline-related adverse reactions. (See WARNINGS.) If concomitant use cannot be avoided, serum levels of theophylline should be monitored and dosage adjustments made as appropriate.

Other Xanthine Derivatives
Some quinolones, including ciprofloxacin, have also been shown to interfere with the metabolism of caffeine. This may lead to reduced clearance of caffeine and a prolongation of its serum half-life. On concurrent administration of ciprofloxacin and caffeine or pentoxifylline containing products, elevated serum concentrations of these xanthine derivatives were reported.

Chelation Complex Formation
Concurrent administration of a quinolone, including ciprofloxacin, with multivalent cation-containing products such as magnesium/aluminum antacids, polymeric phosphate binders (for example. sevelamer, lanthanum carbonate) sucralfate, Videx® (didanosine) chewable/buffered tablets or pediatric powder, other highly buffered drugs, or products containing calcium, iron, or zinc may substantially decrease its absorption, resulting in serum and urine levels considerably lower than desired. (See DOSAGE AND ADMINISTRATIONfor concurrent administration of these agents with ciprofloxacin.)

Histamine H2-receptor antagonists appear to have no significant effect on the bioavailability of ciprofloxacin.

Omeprazole
Concomitant administration of a single tablet dose of 500 mg ciprofloxacin and once-daily administration of 20 mg omeprazole pretreatment for 4 days resulted in a 16% reduction of mean Cmax and mean AUC of ciprofloxacin

Phenytoin
Altered serum levels of phenytoin (increased and decreased) have been reported in patients receiving concomitant ciprofloxacin. To avoid the loss of seizure control associated with decreased phenytoin levels, and to prevent phenytoin overdose-related undesirable effects when ciprofloxacin is discontinued in patients receiving both agents, monitoring of phenytoin therapy, including phenytoin serum concentration measurements, is recommended during and shortly after co-administration of ciprofloxacin with phenytoin.

Oral Antidiabetic Agents
Hypoglycemia has been reported when ciprofloxacin and oral antidiabetic agents, mainly sulfonylureas (for example, glyburide, glimepiride), were co-administered, presumably by intensifying the action of the oral antidiabetic agent (see ADVERSE REACTIONS).The concomitant administration of ciprofloxacin with glyburide has, on rare occasions, resulted in severe hypoglycemia. Fatalities have been reported.

Metronidazole
The serum concentrations of ciprofloxacin and metronidazole were not altered when these two drugs were given concomitantly.

Cyclosporine
Some quinolones, including ciprofloxacin, have been associated with transient elevations in serum creatinine in patients receiving cyclosporine concomitantly.

Oral Anti-coagulants
Simultaneous administration of ciprofloxacin with an oral anticoagulant may augment the effect of the anticoagulant. The risk may vary with the underlying infection, age and general status of the patient so that the contribution of ciprofloxacin to the increase in INR (international normalized ratio) is difficult to assess. Prothrombin time and INR should be monitored frequently during and shortly after co-administration of ciprofloxacin with an oral anticoagulant (for example, warfarin).

Probenecid
Probenecid interferes with renal tubular secretion of ciprofloxacin and produces an increase in the level of ciprofloxacin in the serum. This should be considered if patients are receiving both drugs concomitantly.

Methotrexate
Renal tubular transport of methotrexate may be inhibited by concomitant administration of ciprofloxacin potentially leading to increased plasma levels of methotrexate. This might increase the risk of methotrexate associated toxic reactions. Therefore, patients under methotrexate therapy should be carefully monitored when concomitant ciprofloxacin therapy is indicated.

Metoclopramide
Metoclopramide significantly accelerates the absorption of oral ciprofloxacin resulting in shorter time to reach maximum plasma concentrations. No significant effect was observed on the bioavailability of ciprofloxacin.

Duloxetine
In clinical studies it was demonstrated that concomitant use of duloxetine with strong inhibitors of the CYP450 1A2 isozyme such as fluvoxamine, may result in a 5-fold increase in mean AUC and a 2.5-fold increase in mean Cmax of duloxetine. Although no clinical data are available on a possible interaction with ciprofloxacin, similar effects can be expected upon concomitant administration.

NSAIDs
Non-steroidal anti-inflammatory drugs (but not acetyl salicylic acid) in combination of very high doses of quinolones have been shown to provoke convulsions in pre-clinical studies.

Ropinirole
In a study conducted in 12 patients with Parkinson’s disease who were administered 6 mg ropinirole once daily with 500 mg ciprofloxacin twice-daily, the mean Cmax and mean AUC of ropinirole were increased by 60% and 84%, respectively. Monitoring for ropinirole-related side effects and appropriate dose adjustment of ropinirole is recommended during and shortly after co-administration with ciprofloxacin. (See WARNINGS, Cytochrome P450.)

Lidocaine
In a study conducted in 9 healthy volunteers, concomitant use of 1.5 mg/kg IV lidocaine with 500 mg ciprofloxacin twice daily, resulted in an increase of lidocaine Cmax and AUC by 12% and 26%, respectively. Although lidocaine treatment was well tolerated at this elevated exposure, a possible interaction with ciprofloxacin and an increase in side effects related to lidocaine may occur upon concomitant administration.

Clozapine
Following concomitant administration of 250 mg ciprofloxacin with 304 mg clozapine for 7 days, serum concentrations of clozapine and N-desmethylclozapine were increased by 29% and 31%, respectively. Careful monitoring of clozapine associated adverse effects and appropriate adjustment of clozapine dosage during and shortly after co-administration with ciprofloxacin are advised. (See WARNINGS.)

Sildenafil
Following concomitant administration of a single oral dose of 50 mg sildenafil with 500 mg ciprofloxacin to healthy subjects, the mean Cmax and mean AUC of sildenafil were both increased approximately two-fold. Therefore, sildenafil should be used with caution when co-administered with ciprofloxacin.

Drugs known to prolong QT interval
Precaution should be taken when using ciprofloxacin concomitantly with drugs known to prolong the QT interval (for example, class IA or III antiarrhythmics, tricyclic antidepressants, macrolides, antipsychotics) as ciprofloxacin may have an additive effect on the QT interval (see WARNINGS, Prolongation of the QT Interval and PRECAUTIONS, Geriatric Use).

Carcinogenesis, Mutagenesis, Impairment of Fertility

Eight in vitro mutagenicity tests have been conducted with ciprofloxacin, and the test results are listed below:

Salmonella/Microsome Test (Negative)
E. coli DNA Repair Assay (Negative)
Mouse Lymphoma Cell Forward Mutation Assay (Positive)
Chinese Hamster V79 Cell HGPRT Test (Negative)
Syrian Hamster Embryo Cell Transformation Assay (Negative)
Saccharomyces cerevisiae Point Mutation Assay (Negative)
Saccharomyces cerevisiae Mitotic Crossover and Gene Conversion Assay (Negative)
Rat Hepatocyte DNA Repair Assay (Positive)

Thus, 2 of the 8 tests were positive, but results of the following 3 in vivo test systems gave negative results:

Rat Hepatocyte DNA Repair Assay
Micronucleus Test (Mice)
Dominant Lethal Test (Mice)

Long-term carcinogenicity studies in rats and mice resulted in no carcinogenic or tumorigenic effects due to ciprofloxacin at daily oral dose levels up to 250 and 750 mg/kg to rats and mice, respectively (approximately 1.7- and 2.5- times the highest recommended therapeutic dose based upon mg/m^2).

Results from photo co-carcinogenicity testing indicate that ciprofloxacin does not reduce the time to appearance of UV-induced skin tumors as compared to vehicle control. Hairless (Skh-1) mice were exposed to UVA light for 3.5 hours five times every two weeks for up to 78 weeks while concurrently being administered ciprofloxacin. The time to development of the first skin tumors was 50 weeks in mice treated concomitantly with UVA and ciprofloxacin (mouse dose approximately equal to maximum recommended human dose based upon mg/m^2), as opposed to 34 weeks when animals were treated with both UVA and vehicle. The times to development of skin tumors ranged from 16 to 32 weeks in mice treated concomitantly with UVA and other quinolones.^5

In this model, mice treated with ciprofloxacin alone did not develop skin or systemic tumors. There are no data from similar models using pigmented mice and/or fully haired mice. The clinical significance of these findings to humans is unknown.

Fertility studies performed in rats at oral doses of ciprofloxacin up to 100 mg/kg (approximately 0.7-times the highest recommended therapeutic dose based upon mg/m^2) revealed no evidence of impairment.

Pregnancy

Teratogenic Effects. Pregnancy Category C

There are no adequate and well-controlled studies in pregnant women. Ciprofloxacin should not be used during pregnancy unless the potential benefit justifies the potential risk to both fetus and mother (see WARNINGS). An expert review of published data on experiences with ciprofloxacin use during pregnancy by TERIS - the Teratogen Information System - concluded that therapeutic doses during pregnancy are unlikely to pose a substantial teratogenic risk (quantity and quality of data=fair), but the data are insufficient to state that there is no risk.^9

A controlled prospective observational study followed 200 women exposed to fluoroquinolones (52.5% exposed to ciprofloxacin and 68% first trimester exposures) during gestation.^10 In utero exposure to fluoroquinolones during embryogenesis was not associated with increased risk of major malformations. The reported rates of major congenital malformations were 2.2% for the fluoroquinolone group and 2.6% for the control group (background incidence of major malformations is 1 to 5%). Rates of spontaneous abortions, prematurity and low birth weight did not differ between the groups and there were no clinically significant musculoskeletal dysfunctions up to one year of age in the ciprofloxacin exposed children.

Another prospective follow-up study reported on 549 pregnancies with fluoroquinolone exposure (93% first trimester exposures).^11 There were 70 ciprofloxacin exposures, all within the first trimester. The malformation rates among live-born babies exposed to ciprofloxacin and to fluoroquinolones overall were both within background incidence ranges. No specific patterns of congenital abnormalities were found. The study did not reveal any clear adverse reactions due to in utero exposure to ciprofloxacin.

No differences in the rates of prematurity, spontaneous abortions, or birth weight were seen in women exposed to ciprofloxacin during pregnancy.^9,10 However, these small postmarketing epidemiology studies, of which most experience is from short term, first trimester exposure, are insufficient to evaluate the risk for less common defects or to permit reliable and definitive conclusions regarding the safety of ciprofloxacin in pregnant women and their developing fetuses. Reproduction studies have been performed in rats and mice using oral doses up to 100 mg/kg (0.6 and 0.3 times the maximum daily human dose based upon body surface area, respectively) and have revealed no evidence of harm to the fetus due to ciprofloxacin. In rabbits, oral ciprofloxacin dose levels of 30 and 100 mg/kg (approximately 0.4- and 1.3-times the highest recommended therapeutic dose based upon mg/m^2) produced gastrointestinal toxicity resulting in maternal weight loss and an increased incidence of abortion, but no teratogenicity was observed at either dose level. After intravenous administration of doses up to 20 mg/kg (approximately 0.3-times the highest recommended therapeutic dose based upon mg/m^2) no maternal toxicity was produced and no embryotoxicity or teratogenicity was observed. (See WARNINGS.)

Nursing Mothers

Ciprofloxacin is excreted in human milk. The amount of ciprofloxacin absorbed by the nursing infant is unknown. Because of the potential risk of serious adverse reactions (including articular damage) in infants nursing from mothers taking ciprofloxacin, a decision should be made whether to discontinue nursing or to discontinue the drug, taking into account the importance of the drug to the mother.

Pediatric Use

Ciprofloxacin, like other quinolones, causes arthropathy and histological changes in weight-bearing joints of juvenile animals resulting in lameness. (See ANIMAL PHARMACOLOGY.)

Inhalational Anthrax (Post-Exposure)
Ciprofloxacin is indicated in pediatric patients for inhalational anthrax (post-exposure). The risk-benefit assessment indicates that administration of ciprofloxacin to pediatric patients is appropriate. For information regarding pediatric dosing in inhalational anthrax (post-exposure), see DOSAGE AND ADMINISTRATIONand Inhalational Anthrax, Additional Information.

Complicated Urinary Tract Infection and Pyelonephritis
Ciprofloxacin is indicated for the treatment of complicated urinary tract infections and pyelonephritis due to Escherichia coli. Although effective in clinical trials, ciprofloxacin is not a drug of first choice in the pediatric population due to an increased incidence of adverse events compared to the controls, including events related to joints and/or surrounding tissues. The rates of these events in pediatric patients with complicated urinary tract infection and pyelonephritis within six weeks of follow-up were 9.3% (31/335) versus 6% (21/349) for control agents. The rates of these events occurring at any time up to the one year follow-up were 13.7% (46/335) and 9.5% (33/349), respectively. The rate of all adverse events regardless of drug relationship at six weeks was 41% (138/335) in the ciprofloxacin arm compared to 31% (109/349) in the control arm. (See ADVERSE REACTIONS and CLINICAL STUDIES.)

Cystic Fibrosis
Short-term safety data from a single trial in pediatric cystic fibrosis patients are available. In a randomized, double-blind clinical trial for the treatment of acute pulmonary exacerbations in cystic fibrosis patients (ages 5 to 17 years), 67 patients received ciprofloxacin IV 10 mg/kg/dose q8h for one week followed by ciprofloxacin tablets 20 mg/kg/dose q12h to complete 10 to 21 days treatment and 62 patients received the combination of ceftazidime IV 50 mg/kg/dose q8h and tobramycin IV 3 mg/kg/dose q8h for a total of 10 to 21 days. Patients less than 5 years of age were not studied. Safety monitoring in the study included periodic range of motion examinations and gait assessments by treatment-blinded examiners. Patients were followed for an average of 23 days after completing treatment (range 0 to 93 days). This study was not designed to determine long term effects and the safety of repeated exposure to ciprofloxacin.

Musculoskeletal adverse events in patients with cystic fibrosis were reported in 22% of the patients in the ciprofloxacin group and 21% in the comparison group. Decreased range of motion was reported in 12% of the subjects in the ciprofloxacin group and 16% in the comparison group. Arthralgia was reported in 10% of the patients in the ciprofloxacin group and 11% in the comparison group. Other adverse events were similar in nature and frequency between treatment arms. One of sixty-seven patients developed arthritis of the knee nine days after a ten day course of treatment with ciprofloxacin. Clinical symptoms resolved, but an MRI showed knee effusion without other abnormalities eight months after treatment. However, the relationship of this event to the patient’s course of ciprofloxacin can not be definitively determined, particularly since patients with cystic fibrosis may develop arthralgias/arthritis as part of their underlying disease process.

Geriatric Use

Geriatric patients are at increased risk for developing severe tendon disorders including tendon rupture when being treated with a fluoroquinolone such as ciprofloxacin hydrochloride. This risk is further increased in patients receiving concomitant corticosteroid therapy. Tendinitis or tendon rupture can involve the Achilles, hand, shoulder, or other tendon sites and can occur during or after completion of therapy; cases occurring up to several months after fluoroquinolone treatment have been reported. Caution should be used when prescribing ciprofloxacin hydrochloride to elderly patients especially those on corticosteroids. Patients should be informed of this potential side effect and advised to discontinue ciprofloxacin hydrochloride and contact their healthcare provider if any symptoms of tendinitis or tendon rupture occur (See Boxed Warning, WARNINGS, and ADVERSE REACTIONS/Postmarketing Adverse Event Reports).

In a retrospective analysis of 23 multiple-dose controlled clinical trials of ciprofloxacin encompassing over 3500 ciprofloxacin treated patients, 25% of patients were greater than or equal to 65 years of age and 10% were greater than or equal to 75 years of age. No overall differences in safety or effectiveness were observed between these subjects and younger subjects, and other reported clinical experience has not identified differences in responses between the elderly and younger patients, but greater sensitivity of some older individuals on any drug therapy cannot be ruled out. Ciprofloxacin is known to be substantially excreted by the kidney, and the risk of adverse reactions may be greater in patients with impaired renal function. No alteration of dosage is necessary for patients greater than 65 years of age with normal renal function. However, since some older individuals experience reduced renal function by virtue of their advanced age, care should be taken in dose selection for elderly patients, and renal function monitoring may be useful in these patients. (See CLINICAL PHARMACOLOGYand DOSAGE AND ADMINISTRATION.)

In general, elderly patients may be more susceptible to drug-associated effects on the QT interval. Therefore, precaution should be taken when using ciprofloxacin hydrochloride with concomitant drugs that can result in prolongation of the QT interval (for example, class IA or class III antiarrhythmics) or in patients with risk factors for torsade de pointes (for example, known QT prolongation, uncorrected hypokalemia). (See WARNINGS.)

ADVERSE REACTIONS

Adverse Reactions in Adult Patients

During clinical investigations with oral and parenteral ciprofloxacin, 49,038 patients received courses of the drug. Most of the adverse events reported were described as only mild or moderate in severity, abated soon after the drug was discontinued, and required no treatment. Ciprofloxacin was discontinued because of an adverse event in 1% of orally treated patients.

The most frequently reported drug related events, from clinical trials of all formulations, all dosages, all drug-therapy durations, and for all indications of ciprofloxacin therapy were nausea (2.5%), diarrhea (1.6%), liver function tests abnormal (1.3%), vomiting (1%), and rash (1%).

Additional medically important events that occurred in less than 1% of ciprofloxacin patients are listed below.

BODY AS A WHOLE: headache, abdominal pain/discomfort, foot pain, pain, pain in extremities, injection site reaction (ciprofloxacin intravenous)

CARDIOVASCULAR: palpitation, atrial flutter, ventricular ectopy, syncope, hypertension, angina pectoris, myocardial infarction, cardiopulmonary arrest, cerebral thrombosis, phlebitis, tachycardia, migraine, hypotension

CENTRAL NERVOUS SYSTEM: restlessness, dizziness, lightheadedness, insomnia, nightmares, hallucinations, manic reaction, irritability, tremor, ataxia, convulsive seizures (including status epilepticus), grand mal convulsion, lethargy, drowsiness, weakness, malaise, anorexia, phobia, depersonalization, depression (potentially culminating in self-injurious behavior, such as suicidal ideations/thoughts and attempted or completed suicide), paresthesia, abnormal gait

GASTROINTESTINAL: painful oral mucosa, oral candidiasis, dysphagia, intestinal perforation, gastrointestinal bleeding, cholestatic jaundice, hepatitis

HEMIC/LYMPHATIC: lymphadenopathy, petechia

METABOLIC/NUTRITIONAL: amylase increase, lipase increase, hyperglycemia, hypoglycemia

MUSCULOSKELETAL: arthralgia or back pain, joint stiffness, achiness, neck or chest pain, flare up of gout, muscle weakness

RENAL/UROGENITAL: interstitial nephritis, nephritis, renal failure, polyuria, urinary retention, urethral bleeding, vaginitis, acidosis, breast pain

RESPIRATORY: dyspnea, epistaxis, laryngeal or pulmonary edema, hiccough, hemoptysis, bronchospasm, pulmonary embolism

SKIN/HYPERSENSITIVITY: allergic reaction, pruritus, urticaria, photosensitivity/phototoxicity reaction, flushing, fever, chills, angioedema, edema of the face, neck, lips, conjunctivae or hands, cutaneous candidiasis, hyperpigmentation, erythema nodosum, sweating

SPECIAL SENSES: blurred vision, disturbed vision (change in color perception, overbrightness of lights), decreased visual acuity, diplopia, eye pain, tinnitus, hearing loss, bad taste, chromatopsia

In several instances nausea, vomiting, tremor, irritability, or palpitation were judged by investigators to be related to elevated serum levels of theophylline possibly as a result of drug interaction with ciprofloxacin.

In randomized, double-blind controlled clinical trials comparing ciprofloxacin tablets (500 mg BID) to cefuroxime axetil (250 mg to 500 mg BID) and to clarithromycin (500 mg BID) in patients with respiratory tract infections, ciprofloxacin demonstrated a CNS adverse event profile comparable to the control drugs.

Adverse Reactions in Pediatric Patients

Ciprofloxacin, administered IV and /or orally, was compared to a cephalosporin for treatment of complicated urinary tract infections (cUTI) or pyelonephritis in pediatric patients 1 to 17 years of age (mean age of 6 ± 4 years). The trial was conducted in the US, Canada, Argentina, Peru, Costa Rica, Mexico, South Africa, and Germany. The duration of therapy was 10 to 21 days (mean duration of treatment was 11 days with a range of 1 to 88 days). The primary objective of the study was to assess musculoskeletal and neurological safety within 6 weeks of therapy and through one year of follow-up in the 335 ciprofloxacin- and 349 comparator-treated patients enrolled.

An Independent Pediatric Safety Committee (IPSC) reviewed all cases of musculoskeletal adverse events as well as all patients with an abnormal gait or abnormal joint exam (baseline or treatment-emergent). These events were evaluated in a comprehensive fashion and included such conditions as arthralgia, abnormal gait, abnormal joint exam, joint sprains, leg pain, back pain, arthrosis, bone pain, pain, myalgia, arm pain, and decreased range of motion in a joint. The affected joints included: knee, elbow, ankle, hip, wrist, and shoulder. Within 6 weeks of treatment initiation, the rates of these events were 9.3% (31/335) in the ciprofloxacin-treated group versus 6% (21/349) in comparator-treated patients. The majority of these events were mild or moderate in intensity. All musculoskeletal events occurring by 6 weeks resolved (clinical resolution of signs and symptoms), usually within 30 days of end of treatment. Radiological evaluations were not routinely used to confirm resolution of the events. The events occurred more frequently in ciprofloxacin-treated patients than control patients, regardless of whether they received IV or oral therapy. Ciprofloxacin-treated patients were more likely to report more than one event and on more than one occasion compared to control patients. These events occurred in all age groups and the rates were consistently higher in the ciprofloxacin group compared to the control group. At the end of 1 year, the rate of these events reported at any time during that period was 13.7% (46/335) in the ciprofloxacin-treated group versus 9.5% (33/349) comparator-treated patients.

An adolescent female discontinued ciprofloxacin for wrist pain that developed during treatment. An MRI performed 4 weeks later showed a tear in the right ulnar fibrocartilage. A diagnosis of overuse syndrome secondary to sports activity was made, but a contribution from ciprofloxacin cannot be excluded. The patient recovered by 4 months without surgical intervention.

Findings Involving Joint or Peri-articular Tissues as Assessed by the IPSC
 | Ciprofloxacin | Comparator
All Patients (within 6 weeks) | 31/335 (9.3%) | 21/349 (6%)
95% Confidence Interval* | (-0.8%, +7.2%)
Age Group
≥ 12 months < 24 months | 1/36 (2.8%) | 0/41
≥ 2 years < 6 years | 5/124 (4%) | 3/118 (2.5%)
≥ 6 years < 12 years | 18/143 (12.6%) | 12/153 (7.8%)
≥ 12 years to 17 years | 7/32 (21.9%) | 6/37 (16.2 %)
All Patients (within 1 year) | 46/335 (13.7%) | 33/349 (9.5%)
95% Confidence Interval* | (-0.6%, + 9.1%)
*The study was designed to demonstrate that the arthropathy rate for the ciprofloxacin group did not exceed that of the control group by more than + 6%. At both the 6 week and 1 year evaluations, the 95% confidence interval indicated that it could not be concluded that ciprofloxacin group had findings comparable to the control group.

The incidence rates of neurological events within 6 weeks of treatment initiation were 3% (9/335) in the ciprofloxacin group versus 2% (7/349) in the comparator group and included dizziness, nervousness, insomnia, and somnolence.

In this trial, the overall incidence rates of adverse events regardless of relationship to study drug and within 6 weeks of treatment initiation were 41% (138/335) in the ciprofloxacin group versus 31% (109/349) in the comparator group. The most frequent events were gastrointestinal: 15% (50/335) of ciprofloxacin patients compared to 9% (31/349) of comparator patients. Serious adverse events were seen in 7.5% (25/335) of ciprofloxacin-treated patients compared to 5.7% (20/349) of control patients. Discontinuation of drug due to an adverse event was observed in 3% (10/335) of ciprofloxacin-treated patients versus 1.4% (5/349) of comparator patients. Other adverse events that occurred in at least 1% of ciprofloxacin patients were diarrhea 4.8%, vomiting 4.8%, abdominal pain 3.3%, accidental injury 3%, rhinitis 3%, dyspepsia 2.7%, nausea 2.7%, fever 2.1%, asthma 1.8% and rash 1.8%.

In addition to the events reported in pediatric patients in clinical trials, it should be expected that events reported in adults during clinical trials or postmarketing experience may also occur in pediatric patients.

Postmarketing Adverse Event Reports

The following adverse events have been reported from worldwide marketing experience with fluoroquinolones, including ciprofloxacin. Because these events are reported voluntarily from a population of uncertain size, it is not always possible to reliably estimate their frequency or establish a causal relationship to drug exposure. Decisions to include these events in labeling are typically based on one or more of the following factors: (1) seriousness of the event, (2) frequency of the reporting, or (3) strength of causal connection to the drug.

Acute generalized exanthematous pustulosis (AGEP), Agitation, agranulocytosis, albuminuria, anaphylactic reactions (including life-threatening anaphylactic shock), anosmia, candiduria, cholesterol elevation (serum), confusion, constipation, delirium, dyspepsia, dysphagia, erythema multiforme, exfoliative dermatitis, fixed eruption, flatulence, glucose elevation (blood), hemolytic anemia, hepatic failure (including fatal cases), hepatic necrosis, hyperesthesia, hypertonia, hypesthesia, hypotension (postural), International Normalized Ratio (INR) increased (in patients treated with Vitamin K antagonists), jaundice, marrow depression (life threatening), methemoglobinemia, moniliasis (oral, gastrointestinal, vaginal), myalgia, myasthenia, exacerbation of myasthenia gravis, myoclonus, nystagmus, pancreatitis, pancytopenia (life threatening or fatal outcome), peripheral neuropathy that may be irreversible, phenytoin alteration (serum), photosensitivity/phototoxicity reaction, polyneuropathy, potassium elevation (serum), prothrombin time prolongation or decrease, pseudomembranous colitis (The onset of pseudomembranous colitis symptoms may occur during or after antimicrobial treatment.), psychosis (toxic), QT prolongation, renal calculi, serum sickness like reaction, Stevens-Johnson syndrome, taste loss, tendinitis, tendon rupture, torsade de pointes, toxic epidermal necrolysis (Lyell’s Syndrome), triglyceride elevation (serum), twitching, vaginal candidiasis, vasculitis and ventricular arrhythmia. (See PRECAUTIONS.)

Adverse events were also reported by persons who received ciprofloxacin for anthrax post-exposure prophylaxis following the anthrax bioterror attacks of October 2001. (See also INHALATION ANTHRAX -ADDITIONAL INFORMATION.)

Adverse Laboratory Changes: Changes in laboratory parameters listed as adverse events without regard to drug relationship are listed below:

Hepatic - Elevations of ALT (SGPT) (1.9%), AST (SGOT) (1.7%), alkaline phosphatase (0.8%), LDH (0.4%), serum bilirubin (0.3%).

Hematologic - Eosinophilia (0.6%), leukopenia (0.4%), decreased blood platelets (0.1%), elevated blood platelets (0.1%), pancytopenia (0.1%).

Renal - Elevations of serum creatinine (1.1%), BUN (0.9%), crystalluria, cylindruria, and hematuria have been reported.

Other changes occurring in less than 0.1% of courses were: elevation of serum gammaglutamyl transferase, elevation of serum amylase, reduction in blood glucose, elevated uric acid, decrease in hemoglobin, anemia, bleeding diathesis, increase in blood monocytes, and leukocytosis.

To report SUSPECTED ADVERSE REACTIONS, contact Actavis at 1-800-272-5525 or FDA at 1-800-FDA-1088 or www.fda.gov/medwatch.

OVERDOSAGE

In the event of acute overdosage, reversible renal toxicity has been reported in some cases. The stomach should be emptied by inducing vomiting or by gastric lavage. The patient should be carefully observed and given supportive treatment, including monitoring of renal function, urinary pH and acidify, if required, to prevent crystalluria and administration of magnesium, aluminum, or calcium containing antacids, which can reduce the absorption of ciprofloxacin. Adequate hydration must be maintained. Only a small amount of ciprofloxacin (< 10%) is removed from the body after hemodialysis or peritoneal dialysis.

Single doses of ciprofloxacin were relatively non-toxic via the oral route of administration in mice, rats, and dogs. No deaths occurred within a 14-day post treatment observation period at the highest oral doses tested; up to 5000 mg/kg in either rodent species, or up to 2500 mg/kg in the dog. Clinical signs observed included hypoactivity and cyanosis in both rodent species and severe vomiting in dogs. In rabbits, significant mortality was seen at doses of ciprofloxacin > 2500 mg/kg. Mortality was delayed in these animals, occurring 10 to 14 days after dosing.

In mice, rats, rabbits and dogs, significant toxicity including tonic/clonic convulsions was observed at intravenous doses of ciprofloxacin between 125 and 300 mg/kg.

DOSAGE AND ADMINISTRATION

Adults

Ciprofloxacin tablets should be administered orally to adults as described in the Dosage Guidelines table.

The determination of dosage for any particular patient must take into consideration the severity and nature of the infection, the susceptibility of the causative organism, the integrity of the patient’s host-defense mechanisms, and the status of renal function and hepatic function.

The duration of treatment depends upon the severity of infection. The usual duration is 7 to 14 days; however, for severe and complicated infections more prolonged therapy may be required. Ciprofloxacin should be administered at least 2 hours before or 6 hours after magnesium/aluminum antacids, polymeric phosphate binders (for example, sevelamer, lanthanum carbonate) or sucralfate, Videx® (didanosine) chewable/buffered tablets or pediatric powder for oral solution, other highly buffered drugs, or other products containing calcium, iron or zinc.

ADULT DOSAGE GUIDELINES
Infection | Severity | Dose | Frequency | Usual Durations†
Urinary Tract | Acute Uncomplicated | 250 mg | q 12 h | 3 days
 | Mild/Moderate | 250 mg | q 12 h | 7 to 14 days
 | Severe/Complicated | 500 mg | q 12 h | 7 to 14 days
Chronic Bacterial Prostatitis | Mild/Moderate | 500 mg | q 12 h | 28 days
Lower Respiratory Tract | Mild/Moderate | 500 mg | q 12 h | 7 to 14 days
 | Severe/Complicated | 750 mg | q 12 h | 7 to 14 days
Acute Sinusitis | Mild/Moderate | 500 mg | q 12 h | 10 days
Skin and Skin Structure | Mild/Moderate | 500 mg | q 12 h | 7 to 14 days
 | Severe/Complicated | 750 mg | q 12 h | 7 to 14 days
Bone and Joint | Mild/Moderate | 500 mg | q 12 h | ≥ 4 to 6 weeks
 | Severe/Complicated | 750 mg | q 12 h | ≥ 4 to 6 weeks
Intra-Abdominal* | Complicated | 500 mg | q 12 h | 7 to 14 days
Infectious Diarrhea | Mild/Moderate/Severe | 500 mg | q 12 h | 5 to 7 days
Typhoid Fever | Mild/Moderate | 500 mg | q 12 h | 10 days
Urethral and Cervical Gonococcal Infections | Uncomplicated | 250 mg | single dose | single dose
Inhalational anthrax (post-exposure)** |  | 500 mg | q h 12 | 60 days
* Used in conjunction with metronidazole
† Generally ciprofloxacin tablets should be continued for at least 2 days after the signs and symptoms of infection have disappeared, except for inhalational anthrax (post-exposure).
** Drug administration should begin as soon as possible after suspected or confirmed exposure.

This indication is based on a surrogate endpoint, ciprofloxacin serum concentrations achieved in humans, reasonably likely to predict clinical benefit.^6 For a discussion of ciprofloxacin serum concentrations in various human populations, see Inhalational Anthrax, Additional Information.

Conversion of IV to Oral Dosing in Adults: Patients whose therapy is started with ciprofloxacin hydrochloride I.V. may be switched to ciprofloxacin tablets when clinically indicated at the discretion of the physician (See CLINICAL PHARMACOLOGYand table below for the equivalent dosing regimens).

Equivalent AUC Dosing Regimens
Ciprofloxacin Oral Dosage | Equivalent Ciprofloxacin IV Dosage
250 mg Tablet q 12 h | 200 mg IV q 12 h
500 mg Tablet q 12 h | 400 mg IV q 12 h
750 mg Tablet q 12 h | 400 mg IV q 8 h

Adults with Impaired Renal Function: Ciprofloxacin is eliminated primarily by renal excretion; however, the drug is also metabolized and partially cleared through the biliary system of the liver and through the intestine. These alternative pathways of drug elimination appear to compensate for the reduced renal excretion in patients with renal impairment. Nonetheless, some modification of dosage is recommended, particularly for patients with severe renal dysfunction. The following table provides dosage guidelines for use in patients with renal impairment:

RECOMMENDED STARTING AND MAINTENANCE DOSES
FOR PATIENTS WITH IMPAIRED RENAL FUNCTION
Creatinine Clearance (mL/min) | Dose
> 50 | See Usual Dosage.
30 to 50 | 250 to 500 mg q 12 h
5 to 29 | 250 to 500 mg q 18 h
Patients on hemodialysis or Peritoneal dialysis | 250 to 500 mg q 24 h (after dialysis)

When only the serum creatinine concentration is known, the following formula may be used to estimate creatinine clearance.

Men: Creatinine clearance (mL/min) =

Weight (kg) x (140 - age)

72 x serum creatinine (mg/dL)

Women: 0.85 x the value calculated for men.

The serum creatinine should represent a steady state of renal function.

In patients with severe infections and severe renal impairment, a unit dose of 750 mg may be administered at the intervals noted above. Patients should be carefully monitored.

Pediatrics

Ciprofloxacin tablets should be administered orally as described in the Dosage Guidelines table. An increased incidence of adverse events compared to controls, including events related to joints and/or surrounding tissues, has been observed. (See ADVERSE REACTIONSand CLINICAL STUDIES.)

Dosing and initial route of therapy (that is, IV or oral) for complicated urinary tract infection or pyelonephritis should be determined by the severity of the infection. In the clinical trial, pediatric patients with moderate to severe infection were initiated on 6 to 10 mg/kg IV every 8 hours and allowed to switch to oral therapy (10 to 20 mg/kg every 12 hours), at the discretion of the physician.

PEDIATRIC DOSAGE GUIDELINES

Infection

Route of Administration

Dose (mg/kg)

Frequency

Total Duration

Complicated
Urinary Tract
or
Pyelonephritis
(patients from
1 to 17 years of
age)

Oral

10 mg/kg to 20 mg/kg
(maximum 750 mg per dose; not to be exceeded even in patients weighing > 51 kg)

Every 12 hours

10 to 21 days*

Inhalational Anthrax (Post-Exposure)**

Oral

15 mg/kg
(maximum 500 mg per dose)

Every 12 hours

60 days

* The total duration of therapy for complicated urinary tract infection and pyelonephritis in the clinical trial was determined by the physician. The mean duration of treatment was 11 days (range 10 to 21 days).

** Drug administration should begin as soon as possible after suspected or confirmed exposure to Bacillus anthracis spores. This indication is based on a surrogate endpoint, ciprofloxacin serum concentrations achieved in humans, reasonably likely to predict clinical benefit.^6 For a discussion of ciprofloxacin serum concentrations in various human populations, see Inhalational Anthrax In Adults and Pediatrics, Additional Information.

Pediatric patients with moderate to severe renal insufficiency were excluded from the clinical trial of complicated urinary tract infection and pyelonephritis. No information is available on dosing adjustments necessary for pediatric patients with moderate to severe renal insufficiency (that is, creatinine clearance of < 50 mL/min/1.73m^2).

HOW SUPPLIED

Ciprofloxacin tablets, USP are available as round, white to off-white film-coated tablets containing 250 mg ciprofloxacin. The 250 mg tablet is coded with on one side and “ ” on the other side. Ciprofloxacin tablets, USP are also available as capsule shaped, white to off-white film-coated tablets containing 500 mg or 750 mg ciprofloxacin. The 500 mg tablet is coded with “CR 500” on one side and “ ” on the reverse side. The 750 mg tablet is coded with “CR 750” on one side and “ ” on the reverse side. Ciprofloxacin tablets, USP 250 mg, 500 mg, and 750 mg are available in the following pack types.

 | Strength | NDC Code
Bottles of 100 | 250 mg | NDC 16252-514-01
 | 500 mg | NDC 16252-515-01
Bottles of 50 | 750 mg | NDC 16252-516-05

Store at 20º to 25ºC (68º to 77ºF); excursions permitted to 15º to 30ºC (59º to 86ºF) [see USP Controlled Room Temperature].

ANIMAL PHARMACOLOGY

Ciprofloxacin and other quinolones have been shown to cause arthropathy in immature animals of most species tested. (See WARNINGS.) Damage of weight bearing joints was observed in juvenile dogs and rats. In young beagles, 100 mg/kg ciprofloxacin, given daily for 4 weeks, caused degenerative articular changes of the knee joint. At 30 mg/kg, the effect on the joint was minimal. In a subsequent study in young beagle dogs, oral ciprofloxacin doses of 30 mg/kg and 90 mg/kg ciprofloxacin (approximately 1.3- and 3.5-times the pediatric dose based upon comparative plasma AUCs) given daily for 2 weeks caused articular changes which were still observed by histopathology after a treatment-free period of 5 months. At 10 mg/kg (approximately 0.6-times the pediatric dose based upon comparative plasma AUCs), no effects on joints were observed. This dose was also not associated with arthrotoxicity after an additional treatment-free period of 5 months. In another study, removal of weight bearing from the joint reduced the lesions but did not totally prevent them.

Crystalluria, sometimes associated with secondary nephropathy, occurs in laboratory animals dosed with ciprofloxacin. This is primarily related to the reduced solubility of ciprofloxacin under alkaline conditions, which predominate in the urine of test animals; in man, crystalluria is rare since human urine is typically acidic. In rhesus monkeys, crystalluria without nephropathy was noted after single oral doses as low as 5 mg/kg. (approximately 0.07-times the highest recommended therapeutic dose based upon mg/m^2). After 6 months of intravenous dosing at 10 mg/kg/day, no nephropathological changes were noted; however, nephropathy was observed after dosing at 20 mg/kg/day for the same duration (approximately 0.2-times the highest recommended therapeutic dose based upon mg/m^2).

In dogs, ciprofloxacin at 3 and 10 mg/kg by rapid IV injection (15 sec.) produces pronounced hypotensive effects. These effects are considered to be related to histamine release, since they are partially antagonized by pyrilamine, an antihistamine. In rhesus monkeys, rapid IV injection also produces hypotension but the effect in this species is inconsistent and less pronounced.

In mice, concomitant administration of nonsteroidal anti-inflammatory drugs such as phenylbutazone and indomethacin with quinolones has been reported to enhance the CNS stimulatory effect of quinolones.

Ocular toxicity seen with some related drugs has not been observed in ciprofloxacin-treated animals.

CLINICAL STUDIES

Complicated Urinary Tract Infection and Pyelonephritis – Efficacy in Pediatric Patients:

NOTE: Although effective in clinical trials, ciprofloxacin is not a drug of first choice in the pediatric population due to an increased incidence of adverse events compared to controls, including events related to joints and/or surrounding tissues.

Ciprofloxacin, administered IV and/or orally, was compared to a cephalosporin for treatment of complicated urinary tract infections (cUTI) and pyelonephritis in pediatric patients 1 to 17 years of age (mean age of 6 ± 4 years). The trial was conducted in the US, Canada, Argentina, Peru, Costa Rica, Mexico, South Africa, and Germany. The duration of therapy was 10 to 21 days (mean duration of treatment was 11 days with a range of 1 to 88 days). The primary objective of the study was to assess musculoskeletal and neurological safety.

Patients were evaluated for clinical success and bacteriological eradication of the baseline organism(s) with no new infection or superinfection at 5 to 9 days post-therapy (Test of Cure or TOC). The Per Protocol population had a causative organism(s) with protocol specified colony count(s) at baseline, no protocol violation, and no premature discontinuation or loss to follow-up (among other criteria).

The clinical success and bacteriologic eradication rates in the Per Protocol population were similar between ciprofloxacin and the comparator group as shown below.

Clinical Success and Bacteriologic Eradication at Test of Cure (5 to 9 Days Post-Therapy)
 | Ciprofloxacin | Comparator
Randomized Patients | 337 | 352
Per Protocol Patients | 211 | 231
Clinical Response at 5 to 9 Days Post-Treatment | 95.7% (202/211) | 92.6% (214/231)
 | 95% CI [-1.3%, 7.3%]
Bacteriologic Eradication by Patient at 5 to 9 Days Post-Treatment* | 84.4% (178/211) | 78.3% (181/231)
 | 95% CI [ -1.3%, 13.1%]
Bacteriologic Eradication of the Baseline Pathogen at 5 to 9 Days Post-Treatment
Escherichia coli | 156/178 (88%) | 161/179 (90%)
* Patients with baseline pathogen(s) eradicated and no new infections or superinfections/total number of patients. There were 5.5% (6/211) ciprofloxacin and 9.5% (22/231) comparator patients with superinfections or new infections.

Inhalational Anthrax In Adults And Pediatrics

Additional Information
The mean serum concentrations of ciprofloxacin associated with a statistically significant improvement in survival in the rhesus monkey model of inhalational anthrax are reached or exceeded in adult and pediatric patients receiving oral regimens. (See DOSAGE AND ADMINISTRATION.) Ciprofloxacin pharmacokinetics have been evaluated in various human populations. The mean peak serum concentration achieved at steady-state in human adults receiving 500 mg orally every 12 hours is 2.97 mcg/mL, and 4.56 mcg/mL following 400 mg intravenously every 12 hours. The mean trough serum concentration at steady-state for both of these regimens is 0.2 mcg/mL. In a study of 10 pediatric patients between 6 and 16 years of age, the mean peak plasma concentration achieved is 8.3 mcg/mL and trough concentrations range from 0.09 to 0.26 mcg/mL, following two 30-minute intravenous infusions of 10 mg/kg administered 12 hours apart. After the second intravenous infusion patients switched to 15 mg/kg orally every 12 hours achieve a mean peak concentration of 3.6 mcg/mL after the initial oral dose. Long-term safety data, including effects on cartilage, following the administration of ciprofloxacin to pediatric patients are limited. (For additional information, see PRECAUTIONS, Pediatric Use.) Ciprofloxacin serum concentrations achieved in humans serve as a surrogate endpoint reasonably likely to predict clinical benefit and provide the basis for this indication.^6

A placebo-controlled animal study in rhesus monkeys exposed to an inhaled mean dose of 11 LD50 (~5.5 x 10^5 spores (range 5 to 30 LD50) of B. anthracis was conducted. The minimal inhibitory concentration (MIC) of ciprofloxacin for the anthrax strain used in this study was 0.08 mcg/mL. In the animals studied, mean serum concentrations of ciprofloxacin achieved at expected Tmax (1 hour post-dose) following oral dosing to steady-state ranged from 0.98 to 1.69 mcg/mL. Mean steady-state trough concentrations at 12 hours post-dose ranged from 0.12 to 0.19 mcg/mL.^7 Mortality due to anthrax for animals that received a 30-day regimen of oral ciprofloxacin beginning 24 hours post-exposure was significantly lower (1/9), compared to the placebo group (9/10) [p=0.001]. The one ciprofloxacin-treated animal that died of anthrax did so following the 30-day drug administration period.^8

More than 9300 persons were recommended to complete a minimum of 60 days of antibiotic prophylaxis against possible inhalational exposure to B. anthracis during 2001. Ciprofloxacin was recommended to most of those individuals for all or part of the prophylaxis regimen. Some persons were also given anthrax vaccine or were switched to alternative antibiotics. No one who received ciprofloxacin or other therapies as prophylactic treatment subsequently developed inhalational anthrax. The number of persons who received ciprofloxacin as all or part of their post-exposure prophylaxis regimen is unknown.

Among the persons surveyed by the Centers for Disease Control and Prevention, over 1000 reported receiving ciprofloxacin as sole post-exposure prophylaxis for inhalational anthrax. Gastrointestinal adverse events (nausea, vomiting, diarrhea, or stomach pain), neurological adverse events (problems sleeping, nightmares, headache, dizziness or light headedness) and musculoskeletal adverse events (muscle or tendon pain and joint swelling or pain) were more frequent than had been previously reported in controlled clinical trials. This higher incidence, in the absence of a control group, could be explained by a reporting bias, concurrent medical conditions, other concomitant medications, emotional stress or other confounding factors, and/or a longer treatment period with ciprofloxacin. Because of these factors and limitations in the data collection, it is difficult to evaluate whether the reported symptoms were drug-related.

References:

1. Clinical and Laboratory Standards Institute, Methods for Dilution Antimicrobial Susceptibility Tests for Bacteria That Grow Aerobically; Approved Standard – 9th Edition. CLSI Document M7-A9, CLSI, 950 West Valley Rd., Suite 2500, Wayne, PA, January, 2012.
2. CLSI, Performance Standards for Antimicrobial Disk Susceptibility Tests; Approved Standard – 11 th Edition. CLSI Document M2-A11,CLSI, Wayne, PA, January, 2012.
3. CLSI. Performance Standards for Antimicrobial Susceptibility Testing; 22nd Informational Supplement. CLSI Document M100 S22, January 2012.
4. CLSI. Methods for Antimicrobial Dilution and Disk Susceptibility Testing of Infrequently Isolated or Fastidious Bacteria; Approved Guideline – 2nd Edition. CLSI Document M45 A2, January 2010.
5. Report presented at the FDA’s Anti-Infective Drug and Dermatological Drug Product’s Advisory Committee meeting, March 31, 1993, Silver Spring, MD. Report available from FDA, CDER, Advisors and Consultants Staff, HFD-21, 1901 Chapman Avenue, Room 200, Rockville, MD 20852, USA.
6. 21 CFR 314.510 (Subpart H - Accelerated Approval of New Drugs for Life-Threatening Illnesses).
7. Kelly DJ, et al. Serum concentrations of penicillin, doxycycline, and ciprofloxacin during prolonged therapy in rhesus monkeys. J Infect Dis 1992; 166:1184-7.
8. Friedlander AM, et al. Postexposure prophylaxis against experimental inhalational anthrax. J Infect Dis 1993; 167:1239-42.
9. Friedman J, Polifka J. Teratogenic effects of drugs: a resource for clinicians (TERIS). Baltimore, Maryland: Johns Hopkins University Press, 2000:149-195.
10. Loebstein R, Addis A, Ho E, et al. Pregnancy outcome following gestational exposure to fluoroquinolones: a multicenter prospective controlled study. Antimicrob Agents Chemother. 1998;42(6):1336-1339.
11. Schaefer C, Amoura-Elefant E, Vial T, et al. Pregnancy outcome after prenatal quinolone exposure. Evaluation of a case registry of the European network of teratology information services (ENTIS). Eur J Obstet Gynecol Reprod Biol. 1996;69:83-89.

Brands listed are the trademarks of their respective owners.

Manufactured by:
Watson Pharma Private Limited
Verna, Salcette Goa 403 722 INDIA

Distributed by:
Actavis Pharma, Inc.
Parsippany, NJ 07054 USA

Revised: November 2014

MEDICATION GUIDE
CIPROFLOXACIN (SIP-roe-FLOX-a-sin) TABLETS, USP

Read the Medication Guide that comes with ciprofloxacin tablets before you start taking it and each time you get a refill. There may be new information. This Medication Guide does not take the place of talking to your healthcare provider about your medical condition or your treatment.

What is the most important information I should know about ciprofloxacin tablets?
Ciprofloxacin tablets belong to a class of antibiotics called fluoroquinolones. Ciprofloxacin tablets can cause side effects that may be serious or even cause death. If you get any of the following serious side effects, get medical help right away. Talk with your healthcare provider about whether you should continue to take ciprofloxacin tablets.

1. Tendon rupture or swelling of the tendon (tendinitis)

- Tendon problems can happen in people of all ages who take ciprofloxacin tablets. Tendons are tough cords of tissue that connect muscles to bones. Symptoms of tendon problems may include:
  ● Pain, swelling, tears and inflammation of tendons including the back of the ankle (Achilles), shoulder, hand, or other tendon sites.

- The risk of getting tendon problems while you take ciprofloxacin tablets is higher if you:
  ● Are over 60 years of age
  ● Are taking steroids (corticosteroids)
  ● Have had a kidney, heart or lung transplant

- Tendon problems can happen in people who do not have the above risk factors when they take ciprofloxacin tablets. Other reasons that can increase your risk of tendon problems can include:
  ● Physical activity or exercise
  ● Kidney failure
  ●Tendon problems in the past, such as in people with rheumatoid arthritis (RA)

- Call your healthcare provider right away at the first sign of tendon pain, swelling or inflammation. Stop taking ciprofloxacin tablets until tendinitis or tendon rupture has been ruled out by your healthcare provider. Avoid exercise and using the affected area. The most common area of pain and swelling is the Achilles tendon at the back of your ankle. This can also happen with other tendons.

- Talk to your healthcare provider about the risk of tendon rupture with continued use of ciprofloxacin tablets. You may need a different antibiotic that is not a fluoroquinolone to treat your infection.

- Tendon rupture can happen while you are taking or after you have finished taking ciprofloxacin tablets. Tendon ruptures have happened up to several months after patients have finished taking their fluoroquinolone.

- Get medical help right away if you get any of the following signs or symptoms of a tendon rupture:
  ● Hear or feel a snap or pop in a tendon area
  ● Bruising right after an injury in a tendon area
  ● Unable to move the affected area or bear weight

2. Worsening of myasthenia gravis (a disease which causes muscle weakness).

Fluoroquinolones like ciprofloxacin may cause worsening of myasthenia gravis symptoms, including muscle weakness and breathing problems. Call your healthcare provider right away if you have any worsening muscle weakness or breathing problems.

See the section “What are the possible side effects of ciprofloxacin tablets?” for more information about side effects.

What are ciprofloxacin tablets?
Ciprofloxacin tablets are fluoroquinolone antibiotic medicine used to treat certain infections caused by certain germs called bacteria.

Children less than 18 years of age have a higher chance of getting bone, joint, or tendon (musculoskeletal) problems such as pain or swelling while taking ciprofloxacin tablets. Ciprofloxacin tablets should not be used as the first choice of antibiotic medicine in children under 18 years of age.

Ciprofloxacin tablets should not be used in children under 18 years old, except to treat specific serious infections, such as complicated urinary tract infections and to prevent anthrax disease after breathing the anthrax bacteria germ (inhalational exposure).

Sometimes infections are caused by viruses rather than by bacteria. Examples include viral infections in the sinuses and lungs, such as the common cold or flu. Antibiotics, including ciprofloxacin tablets, do not kill viruses.

Call your healthcare provider if you think your condition is not getting better while you are taking ciprofloxacin tablets.

Who should not take ciprofloxacin tablets?
Do not take ciprofloxacin tablets if you:

- Have ever had a severe allergic reaction to an antibiotic known as a fluoroquinolone, or are allergic to any of the ingredients in ciprofloxacin tablets. Ask your healthcare provider if you are not sure. See the list of ingredients in ciprofloxacin tablets at the end of this Medication Guide.
- Also take a medicine called tizanidine (Zanaflex®). Serious side effects from tizanidine are likely to happen.

What should I tell my healthcare provider before taking ciprofloxacin tablets?
See “What is the most important information I should know about ciprofloxacin tablets?”

Tell your healthcare provider about all your medical conditions, including if you:

- Have tendon problems.
- Have a disease that causes muscle weakness (myasthenia gravis).
- Have central nervous system problems (such as epilepsy).
- Have nerve problems.
- Have or anyone in your family has an irregular heartbeat, especially a condition called “QT prolongation”.
- Have a history of seizures.
- Have kidney problems. You may need a lower dose of ciprofloxacin tablets if your kidneys do not work well.
- Have rheumatoid arthritis (RA) or other history of joint problems.
- Have trouble swallowing pills.
- Are pregnant or planning to become pregnant. It is not known if ciprofloxacin tablets will harm your unborn child.
- Are breast-feeding or planning to breast-feed. Ciprofloxacin passes into breast milk. You and your healthcare provider should decide whether you will take ciprofloxacin tablets or breast-feed.

Tell your healthcare provider about all the medicines you take, including prescription and non-prescription medicines, vitamins and herbal and dietary supplements. Ciprofloxacin tablets and other medicines can affect each other causing side effects. Especially tell your healthcare provider if you take:

- An NSAID (Non-Steroidal Anti-Inflammatory Drug). Many common medicines for pain relief are NSAIDs. Taking an NSAID while you take ciprofloxacin tablets or other fluoroquinolones may increase your risk of central nervous system effects and seizures. See “What are the possible side effects of ciprofloxacin tablets?.”
- A blood thinner (such as warfarin, Coumadin®, Jantoven®).
- Tizanidine (Zanaflex®). You should not take ciprofloxacin tablets if you are already taking tizanidine. See “Who should not take ciprofloxacin tablets?”.
- Theophylline (such as Theo-24®, Elixophyllin®, Theochron®, Uniphyl®, Theolair®).
- Glyburide (Micronase®, Glynase®, Diabeta®, Glucovance®). See “What are the possible side effects of ciprofloxacin tablets?”.
- Phenytoin (Fosphenytoin Sodium®, Cerebyx®, Dilantin-125®, Dilantin®, Extended Phenytoin Sodium®, Prompt Phenytoin Sodium®, Phenytek®).
- Products that contain caffeine.
- A medicine to control your heart rate or rhythm (antiarrhythmics) See “What are the possible side effects of ciprofloxacin tablets?”.
- An anti-psychotic medicine.
- A tricyclic antidepressant.
- A water pill (diuretic).
- A steroid medicine. Corticosteroids taken by mouth or by injection may increase the chance of tendon injury. See “What is the most important information I should know about ciprofloxacin tablets?”.
- Methotrexate (Trexall®)
- Probenecid (Probalan®, Col-probenecid®).
- Metoclopromide (Reglan®, Reglan ODT®).
- Ropinirole (Requip®).
- Lidocaine (Xylocaine® intravenous infusion).
- Clozapine (Clozaril®, Fazaclo® ODT®).
- Pentoxifylline (Trental®).
- Sildenafil (Viagra®, Revatio®).
- Cyclosporine (Gengraf®, Neoral®, Sandimmune®, Sangcya®).
- Omeprazole.
- Certain medicines may keep ciprofloxacin tablets from working correctly. Take ciprofloxacin tablets either 2 hours before or 6 hours after taking these products:
  ● An antacid, multivitamin, or other product that has magnesium, calcium, aluminum, iron, or zinc.
  ● Sucralfate (Carafate®).
  ● Didanosine (Videx®, Videx EC®).

Ask your healthcare provider if you are not sure if any of your medicines are listed above.

Know the medicines you take. Keep a list of your medicines and show it to your healthcare provider and pharmacist when you get a new medicine.

How should I take ciprofloxacin tablets?

- Take ciprofloxacin tablets exactly as prescribed by your healthcare provider.
- Take ciprofloxacin tablets in the morning and evening at about the same time each day. Swallow the tablet whole. Do not split, crush or chew the tablet. Tell your healthcare provider if you can not swallow the tablet whole.
- Ciprofloxacin tablets can be taken with or without food.
- Ciprofloxacin tablets should not be taken with dairy products (like milk or yogurt) or calcium-fortified juices alone, but may be taken with a meal that contains these products.
- Drink plenty of fluids while taking ciprofloxacin tablets.
- Do not skip any doses, or stop taking ciprofloxacin tablets even if you begin to feel better, until you finish your prescribed treatment, unless:
  ● You have tendon effects (see “What is the most important information I should know about ciprofloxacin tablets?”),
  ● You have a serious allergic reaction (see “What are the possible side effects of ciprofloxacin tablets?”), or
  ● Your healthcare provider tells you to stop.

This will help make sure that all of the bacteria are killed and lower the chance that the bacteria will become resistant to ciprofloxacin tablets. If this happens, ciprofloxacin tablets and other antibiotic medicines may not work in the future.

- If you miss a dose of ciprofloxacin tablets, take it as soon as you remember. Do not take two doses at the same time, and do not take more than two doses in one day.
- If you take too much, call your healthcare provider or get medical help immediately.

If you have been prescribed ciprofloxacintablets after being exposed to anthrax:

- Ciprofloxacin tablets have been approved to lessen the chance of getting anthrax disease or worsening of the disease after you are exposed to the anthrax bacteria germ.
- Take ciprofloxacin tablets exactly as prescribed by your healthcare provider. Do not stop taking ciprofloxacin tablets without talking with your healthcare provider. If you stop taking ciprofloxacin tablets too soon, it may not keep you from getting the anthrax disease.
- Side effects may happen while you are taking ciprofloxacin tablets. When taking your ciprofloxacin tablets to prevent anthrax infection, you and your healthcare provider should talk about whether the risks of stopping ciprofloxacin tablets too soon are more important than the risks of side effects with ciprofloxacin tablets.
- If you are pregnant, or plan to become pregnant while taking ciprofloxacin tablets, you and your healthcare provider should decide whether the benefits of taking ciprofloxacin tablets for anthrax are more important than the risks.

What should I avoid while taking ciprofloxacin tablets?

- Ciprofloxacin tablets can make you feel dizzy and lightheaded. Do not drive, operate machinery, or do other activities that require mental alertness or coordination until you know how ciprofloxacin tablets affect you.
- Avoid sunlamps, tanning beds, and try to limit your time in the sun. Ciprofloxacin tablets can make your skin sensitive to the sun (photosensitivity) and the light from sunlamps and tanning beds. You could get severe sunburn, blisters or swelling of your skin. If you get any of these symptoms while taking ciprofloxacin tablets, call your healthcare provider right away. You should use a sunscreen and wear a hat and clothes that cover your skin if you have to be in sunlight.

What are the possible side effects of ciprofloxacin tablets?

○ Ciprofloxacin tablets can cause side effects that may be serious or even cause death. See “What is the most important information I should know about ciprofloxacin tablets?”

Other serious side effects of ciprofloxacin tablets include:

- Theophylline

You may have serious seizure and breathing problems when you take theophylline with ciprofloxacin tablets. These problems may lead to death. Get emergency help right away if you have seizures or trouble breathing.

- Central Nervous System effects

Seizures have been reported in people who take fluoroquinolone antibiotics including ciprofloxacin tablets. Tell your healthcare provider if you have a history of seizures. Ask your healthcare provider whether taking ciprofloxacin tablets will change your risk of having a seizure.

Central Nervous System (CNS) side effects may happen as soon as after taking the first dose of ciprofloxacin tablets. Talk to your healthcare provider right away if you get any of these side effects, or other changes in mood or behavior:

- Feel dizzy
- Seizures
- Hear voices, see things, or sense things that are not there (hallucinations)
- Feel restless
- Tremors
- Feel anxious or nervous
- Confusion
- Depression
- Trouble sleeping
- Nightmares
- Feel more suspicious (paranoia)
- Suicidal thoughts or acts

- Serious allergic reactions

Allergic reactions, including death, can happen in people taking fluoroquinolones, including ciprofloxacin tablets, even after only one dose. Stop taking ciprofloxacin tablets and get emergency medical help right away if you get any of the following symptoms of a severe allergic reaction:

- Hives.
- Trouble breathing or swallowing.
- Swelling of the lips, tongue, face.
- Throat tightness, hoarseness.
- Rapid heartbeat.
- Faint.
- Yellowing of the skin or eyes. Stop taking ciprofloxacin tablets and tell your healthcare provider right away if you get yellowing of your skin or white part of your eyes, or if you have dark urine. These can be signs of a serious reaction to ciprofloxacin tablets (a liver problem).
- Skin rash

Skin rash may happen in people taking ciprofloxacin tablets, even after only one dose. Stop taking ciprofloxacin tablets at the first sign of a skin rash and call your healthcare provider. Skin rash may be a sign of a more serious reaction to ciprofloxacin tablets.

- Serious heart rhythm changes (QT prolongation and torsade de pointes)

Tell your healthcare provider right away if you have a change in your heart beat (a fast or irregular heartbeat), or if you faint. Ciprofloxacin tablets may cause a rare heart problem known as prolongation of the QT interval. This condition can cause an abnormal heartbeat and can be very dangerous. The chances of this event are higher in people:

- Who are elderly
- With a family history of prolonged QT interval
- With low blood potassium (hypokalemia)
- Who take certain medicines to control heart rhythm (antiarrhythmics)

- Intestine infection (Pseudomembranous colitis)

Pseudomembranous colitis can happen with most antibiotics, including ciprofloxacin tablets. Call your healthcare provider right away if you get watery diarrhea, diarrhea that does not go away, or bloody stools. You may have stomach cramps and a fever. Pseudomembranous colitis can happen 2 or more months after you have finished your antibiotic.

- Changes in sensation and nerve damage (Peripheral Neuropathy)

Damage to the nerves in arms, hands, legs, or feet can happen in people who take fluoroquinolones, including ciprofloxacin tablets. Stop ciprofloxacin tablets and talk with your healthcare provider right away if you get any of the following symptoms of peripheral neuropathy in your arms, hands, legs, or feet:

- Pain
- Burning
- Tingling
- Numbness
- Weakness

The nerve damage may be permanent.

- Low blood sugar (hypoglycemia)

People who take ciprofloxacin tablets and other fluoroquinolone medicines with the oral anti-diabetes medicine glyburide (Micronase, Glynase, Diabeta, Glucovance) can get low blood sugar (hypoglycemia) which can sometimes be severe. Tell your healthcare provider if you get low blood sugar with ciprofloxacin tablets. Your antibiotic medicine may need to be changed.

- Sensitivity to sunlight (photosensitivity). See “What should I avoid while taking ciprofloxacin tablets?”
- Joint Problems

Increased chance of problems with joints and tissues around joints in children under 18 years old. Tell your child’s healthcare provider if your child has any joint problems during or after treatment with ciprofloxacin tablets.

The most common side effects of ciprofloxacin tablets include:

- Nausea
- Diarrhea
- Changes in liver function tests
- Vomiting
- Rash
- Vaginal yeast infection
- Pain or discomfort in the abdomen
- Headache

These are not all the possible side effects of ciprofloxacin tablets. Tell your healthcare provider about any side effect that bothers you, or that does not go away.

Call your doctor for medical advice about side effects. You may report side effects to FDA at 1-800-FDA-1088.

How should I store ciprofloxacin tablets?

- Ciprofloxacin tablets
- Store ciprofloxacin tablets at 20°-25°C (68°-77°F); excursions permitted to 15°-30°C (59°-86°F).

Keep ciprofloxacin tablets and all medicines out of the reach of children.

General Information about Ciprofloxacin Tablets
Medicines are sometimes prescribed for purposes other than those listed in a Medication Guide. Do not use ciprofloxacin tablets for a condition for which it is not prescribed. Do not give ciprofloxacin tablets to other people, even if they have the same symptoms that you have. It may harm them.

This Medication Guide summarizes the most important information about ciprofloxacin tablets. If you would like more information about ciprofloxacin tablets, talk with your healthcare provider. You can ask your healthcare provider or pharmacist for information about ciprofloxacin tablets that is written for healthcare professionals. For more information call 1-800-272-5525.

What are the ingredients in ciprofloxacin tablets?

- Ciprofloxacin tablets:
- Active ingredient: ciprofloxacin
- Inactive ingredients: cornstarch, microcrystalline cellulose, silicon dioxide, crospovidone, magnesium stearate, polyvinyl alcohol, talc, titanium dioxide, polyethylene glycol and purified water

This Medication Guide has been approved by the U.S. Food and Drug Administration.

Brands listed are the trademarks of their respective owners.

Manufactured by:
Watson Pharma Private Limited
Verna, Salcette Goa 403 722 INDIA

Distributed by:
Actavis Pharma, Inc.
Parsippany, NJ 07054 USA

Revised: November 2014

Principal Display Panel

Ciprofloxacin Tablets, USP 250mg
6 Tablets
NDC 10544-147-06